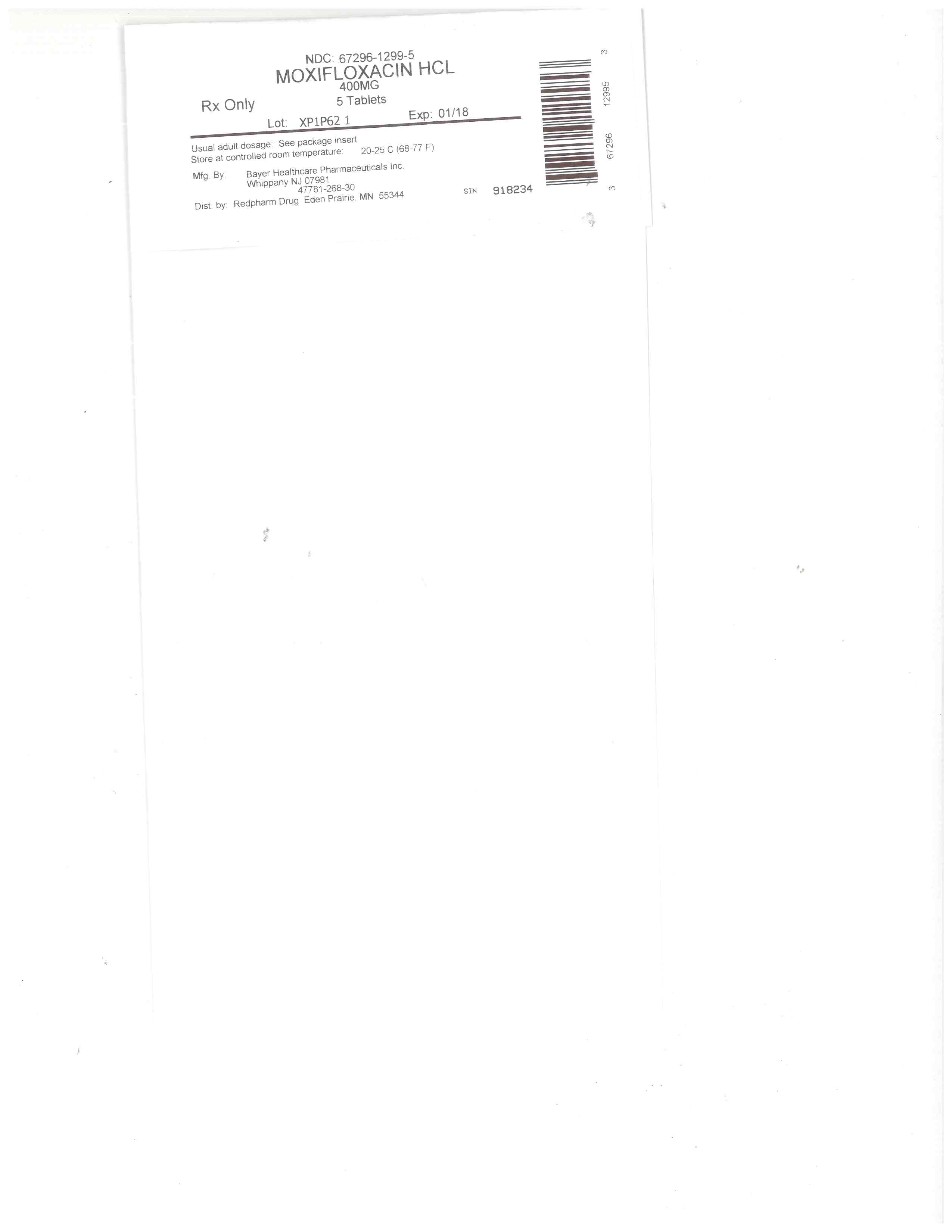 DRUG LABEL: Moxifloxacin Hydrochloride
NDC: 67296-1299 | Form: TABLET, FILM COATED
Manufacturer: RedPharm Drug, Inc.
Category: prescription | Type: HUMAN PRESCRIPTION DRUG LABEL
Date: 20200120

ACTIVE INGREDIENTS: MOXIFLOXACIN HYDROCHLORIDE 400 mg/1 1
INACTIVE INGREDIENTS: LACTOSE MONOHYDRATE; HYPROMELLOSES; TITANIUM DIOXIDE; POLYETHYLENE GLYCOL, UNSPECIFIED; FERRIC OXIDE RED; CELLULOSE, MICROCRYSTALLINE; CROSCARMELLOSE SODIUM; MAGNESIUM STEARATE

BOXED WARNING

WARNING: SERIOUS ADVERSE REACTIONS INCLUDING TENDINITIS, TENDON RUPTURE, PERIPHERAL NEUROPATHY, CENTRAI NERVOUS SYTEM EFFECTS AND EXACERBATION OF MYASTHENIA GRAVIS

•
Fluoroquinolones, including Moxifloxacin Hydrochloride, have been associated with disabling and potentially irreversible serious adverse reactions that have occurred together [see Warnings and Precautions (5.1)], including:

o
Tendinitis and tendon rupture [see Warnings and Precautions (5.2)]
o
Peripheral neuropathy [see Warnings and Precautions (5.3)]
o
Central nervous system effects [see Warnings and Precautions (5.4)]

Discontinue Moxifloxacin Hydrochloride immediately and avoid the use of fluoroquinolones, including Moxifloxacin Hydrochloride, in patients who experience any of these serious adverse reactions [see Warnings and Precautions (5.1)].
•
Fluoroquinolones, including Moxifloxacin Hydrochloride, may exacerbate muscle weakness in patients with myasthenia gravis. Avoid Moxifloxacin Hydrochloride in patients with known history of myasthenia gravis [see Warnings and Precautions (5.5)].
•
Because fluoroquinolones, including Moxifloxacin Hydrochloride, have been associated with serious adverse reactions [see Warnings and Precautions (5.1-5.13)], reserve Moxifloxacin Hydrochloride for use in patients who have no alternative treatment options for the following indications:
o
Acute bacterial sinusitis [see Indications and Usage (1.6)]
o
Acute bacterial exacerbation of chronic bronchitis [see Indications and Usage (1.7)]

HIGHLIGHTS OF PRESCRIBING INFORMATION

These highlights do not include all the information needed to use MOXIFLOXACIN HYDROCHLORIDE safely and effectively. See full prescribing information for MOXIFLOXACIN HYDROCHLORIDE
MOXIFLOXACIN HYDROCHLORIDE tablets, for oral use
Initial U.S. Approval: 1999

WARNING: SERIOUS ADVERSE REACTIONS INCLUDING TENDINITIS, TENDON RUPTURE, PERIPHERAL NEUROPATHY, CENTRIAL NERVOUS SYSTEM EFFECTS AND EXACERBATION OF MYASTHENIA GRAVIS
SEE FULL PRESCRIBING INFORMATION FOR COMPLETE BOXED WARNING.

Fluoroquinolones, including Moxifloxacin Hydrochloride, have been associated with disabling and potentially irreversible serious adverse reactions that have occurred together (5.1) including:

o
Tendinitis and tendon rupture (5.2)
o
Peripheral Neuropathy (5.3)
o
Central nervous system effects (5.4)

Discontinue Moxifloxacin Hydrochloride immediately and avoid the use of fluoroquinolones, including Moxifloxacin Hydrochloride, in patients who experience any of these serious adverse reactions (5.1)
•
Fluoroquinolones, including Moxifloxacin Hydrochloride, may exacerbate muscle weakness in patients with myasthenia gravis. Avoid Moxifloxacin Hydrochloride in patients with known history of myasthenia gravis (5.5).
•
Because fluoroquinolones, including Moxifloxacin Hydrochloride, have been associated with serious adverse reactions (5.1–5.13), reserve Moxifloxacin Hydrochloride for use in patients who have no alternative treatment options for the following indications:

o
Acute bacterial sinusitis (1.6)

Acute bacterial exacerbation of chronic bronchitis (1.7)

RECENT MAJOR CHANGES

Boxed Warning 7/2016

Indications and Usage, Acute Bacterial Sinusitis (1.6) 7/2016

Indications and Usage, Acute Bacterial Exacerbation of Chronic
Bronchitis (1.7) 7/2016

Dosage and Administration, Dosage in Adult Patients (2.1) 7/2016

Warnings and Precautions (5)

INDICATIONS AND USAGE

Moxifloxacin Hydrochloride is a fluoroquinolone antibacterial indicated for treating infections in adults 18 years of age and older caused by designated susceptible bacteria, in the conditions listed below:

•
Community Acquired Pneumonia (1.1)
•
Skin and Skin Structure Infections: Uncomplicated (1.2) and Complicated (1.3)
•
Complicated Intra-Abdominal Infections (1.4)
•
Plague (1.5)
•
Acute Bacterial Sinusitis (1.6)
•
Acute Bacterial Exacerbation of Chronic Bronchitis (1.7)

To reduce the development of drug-resistant bacteria and maintain the effectiveness of Moxifloxacin Hydrochloride and other antibacterial drugs. Moxifloxacin Hydrochloride should be used only to treat or prevent infections that are proven or strongly suspected to be caused by susceptible bacteria. (1.8)

DOSAGE AND ADMINISTRATION

Type of Infection

Dose Every 24 hours

Duration

(days)

Community Acquired Pneumonia (1.1)

400 mg

7–14

Uncomplicated Skin and Skin Structure Infections (SSSI) (1.2)

400 mg

7

Complicated SSSI (1.3)

400 mg

7–21

Complicated Intra-Abdominal Infections (1.4)

400 mg

5–14

Plague (1.5)

400 mg

10–14

Acute Bacterial Sinusitis (1.6)

400 mg

10

Acute Bacterial Exacerbation of Chronic Bronchitis (1.7)

400 mg

5

•
No dosage adjustment in patients with renal or hepatic impairment. (8.6, 8.7)
•
Do not mix with other medications in intravenous bag or in an intravenous line. (2.3)

DOSAGE FORMS AND STRENGTHS

•
Tablets: Moxifloxacin hydrochloride (equivalent to 400 mg moxifloxacin) (3.1)

CONTRAINDICATIONS

Known hypersensitivity to Moxifloxacin Hydrochloride or other quinolones (4, 5.8)

WARNINGS AND PRECAUTIONS

•
Prolongation of the QT interval and isolated cases of torsade de pointes has been reported. Avoid use in patients with known prolongation, proarrhythmic conditions such as clinically significant bradycardia or acute myocardial ischemia, hypokalemia, hypomagnesemia, and with drugs that prolong the QT interval. (5.6, 7.5, 8.5)
•
Hypersensitivity and other serious reactions: Serious and sometimes fatal reactions, including anaphylactic reactions, may occur after first or subsequent doses of Moxifloxacin Hydrochloride. Discontinue Moxifloxacin Hydrochloride at first sign of skin rash, jaundice or any other sign of hypersensitivity. (5.7, 5.8)
•
Clostridium difficile-Associated Diarrhea: Evaluate if diarrhea occurs. (5.9)

ADVERSE REACTIONS

Most common reactions (3% or greater) were nausea, diarrhea, headache, and dizziness. (6)

To report SUSPECTED ADVERSE REACTIONS, contact

To report SUSPECTED ADVERSE REACTIONS, contact Alvogen at 1-866-770-3024 or FDA at 1-800-FDA-1088 or WWW.FDA.GOV/MEDWATCH.

DRUG INTERACTIONS

Interacting Drug

Interaction

Multivalent cation-containing products including: antacids, sucralfate, multivitamins

Decreased Moxifloxacin Hydrochloride absorption. Take Moxifloxacin Hydrochloride Tablet at least 4 hours before or 8 hours after these products. (2.2, 7.1, 12.3)

Warfarin

Anticoagulant effect enhanced. Monitor prothrombin time/INR, and bleeding. (6, 7.2, 12.3)

Class IA and Class III antiarrhythmics:

Proarrhythmic effect may be enhanced. Avoid concomitant use. (5.6, 7.5)

Antidiabetic agents

Carefully monitor blood glucose. (5.11, 7.3)

USE IN SPECIFIC POPULATIONS

•
Pregnancy: Based on animal data may cause fetal harm. (8.1)
•
Geriatrics: Increased risk for severe tendon disorders further increased by concomitant corticosteroid therapy and increased risk of prolongation of the QT interval. (5.1, 5.6, 8.5)

See 17 for PATIENT COUNSELING INFORMATION and Medication Guide.

Revised: 9/2016

FULL PRESCRIBING INFORMATION: CONTENTS*

WARNING: SERIOUS ADVERSE REACTIONS INCLUDING TENDINITIS, TENDON RUPTURE, PERIPHERAL NEUROPATHY, CENTRAI NERVOUS SYTEM EFFECTS AND EXACERBATION OF MYASTHENIA GRAVIS
1 INDICATIONS AND USAGE
1.1 Community Acquired Pneumonia
1.2 Uncomplicated Skin and Skin Structure Infections
1.3 Complicated Skin and Skin Structure Infections
1.4 Complicated Intra-Abdominal Infections
1.5 Plague
1.6 Acute Bacterial Sinusitis
1.7 Acute Bacterial Exacerbation of Chronic Bronchitis
1.8 Usage
2 DOSAGE AND ADMINISTRATION
2.1 Dosage in Adult Patients
2.2 Important Administration Instructions
3 DOSAGE FORMS AND STRENGTHS
4 CONTRAINDICATIONS
5 WARNINGS AND PRECAUTIONS
5.1 Disabling and Potentially Irreversible Serious Adverse Reactions Including Tendinitis and Tendon Rupture, Peripheral Neuropathy, and Central Nervous System Effects
5.2 Tendinitis and Tendon Rupture
5.3 Peripheral Neuropathy
5.4 Central Nervous System Effects
5.5 Exacerbation of Myasthenia Gravis
5.6 QT Prolongation
5.7 Other Serious and Sometimes Fatal Adverse Reactions
5.8 Hypersensitivity Reactions
5.9 Clostridium difficile-Associated Diarrhea
5.10 Arthropathic Effects in Animals
5.11 Blood Glucose Disturbances
5.12 Photosensitivity/Phototoxicity
5.13 Development of Drug Resistant Bacteria
6 ADVERSE REACTIONS
6.1 Clinical Trials Experience
6.2 Postmarketing Experience
7 DRUG INTERACTIONS
7.1 Antacids, Sucralfate, Multivitamins and other Products Containing Multivalent Cations
7.2 Warfarin
7.3 Antidiabetic Agents
7.4 Nonsteroidal Anti-Inflammatory Drugs
7.5 Drugs that Prolong QT
8 USE IN SPECIFIC POPULATIONS
8.1 Pregnancy
8.2 Lactation
8.4 Pediatric Use
8.5 Geriatric Use
8.6 Renal Impairment
8.7 Hepatic Impairment
10 OVERDOSAGE
11 DESCRIPTION
12 CLINICAL PHARMACOLOGY
12.1 Mechanism of Action
12.2 Pharmacodynamics
12.3 Pharmacokinetics
12.4 Microbiology
13 NONCLINICAL TOXICOLOGY
13.1 Carcinogenesis, Mutagenesis, Impairment of Fertility
13.2 Animal Toxicology and/or Pharmacology
14 CLINICAL STUDIES
14.1 Acute Bacterial Sinusitis
14.2 Acute Bacterial Exacerbation of Chronic Bronchitis
14.3 Community Acquired Pneumonia
14.4 Uncomplicated Skin and Skin Structure Infections
14.5 Complicated Skin and Skin Structure Infections
14.6 Complicated Intra-Abdominal Infections
14.7 Plague
15 REFERENCES
16 HOW SUPPLIED/STORAGE AND HANDLING
17 PATIENT COUNSELING INFORMATION

*
Sections or subsections omitted from the full prescribing information are not listed.

1 INDICATIONS AND USAGE

1.1 Community Acquired Pneumonia

Moxifloxacin Hydrochloride is indicated in adult patients for the treatment of Community Acquired Pneumonia caused by susceptible isolates of Streptococcus pneumoniae (including multi-drug resistant Streptococcus pneumoniae [MDRSP]), Haemophilus influenzae, Moraxella catarrhalis, methicillin-susceptible Staphylococcus aureus, Klebsiella pneumoniae, Mycoplasma pneumoniae, or Chlamydophila pneumoniae [see Clinical Studies (14.3)].

MDRSP isolates are isolates resistant to two or more of the following antibacterial drugs: penicillin (minimum inhibitory concentrations [MIC] ≥ 2 mcg/mL), 2nd generation cephalosporins (for example, cefuroxime), macrolides, tetracyclines, and trimethoprim/sulfamethoxazole.

1.2 Uncomplicated Skin and Skin Structure Infections

Moxifloxacin Hydrochloride is indicated in adult patients for the treatment of Uncomplicated Skin and Skin Structure Infections caused by susceptible isolates of methicillin-susceptible Staphylococcus aureus or Streptococcus pyogenes [see Clinical Studies (14.4)].

1.3 Complicated Skin and Skin Structure Infections

Moxifloxacin Hydrochloride is indicated in adult patients for the treatment of Complicated Skin and Skin Structure Infections caused by susceptible isolates of methicillin-susceptible Staphylococcus aureus, Escherichia coli, Klebsiella pneumoniae, or Enterobacter cloacae[see Clinical Studies (14.5)].

1.4 Complicated Intra-Abdominal Infections

Moxifloxacin Hydrochloride is indicated in adult patients for the treatment of Complicated Intra-Abdominal Infections (cIAI) including polymicrobial infections such as abscess caused by susceptible isolates of Escherichia coli, Bacteroides fragilis, Streptococcus anginosus, Streptococcus constellatus, Enterococcus faecalis, Proteus mirabilis, Clostridium perfringens, Bacteroides thetaiotaomicron, or Peptostreptococcus species [see Clinical Studies (14.6)].

1.5 Plague

Moxifloxacin Hydrochloride is indicated in adult patients for the treatment of plague, including pneumonic and septicemic plague, due to susceptible isolates of Yersinia pestis and prophylaxis of plague in adult patients. Efficacy studies of moxifloxacin could not be conducted in humans with plague for feasibility reasons. Therefore this indication is based on an efficacy study conducted in animals only [see Clinical Studies (14.7)].

1.6 Acute Bacterial Sinusitis

Moxifloxacin Hydrochloride is indicated in adult patients (18 years of age and older) for the treatment of acute bacterial sinusitis (ABS) caused by susceptible isolates of Streptococcus pneumoniae, Haemophilus influenzae, or Moraxella catarrhalis [see Clinical Studies (14.1)].

Because fluoroquinolones, including Moxifloxacin Hydrochloride, have been associated with serious adverse reactions [see Warnings and Precautions (5.1-5.13)] and for some patients ABS is self-limiting, reserve Moxifloxacin Hydrochloride for treatment of ABS in patients who have no alternative treatment options.

1.7 Acute Bacterial Exacerbation of Chronic Bronchitis

Moxifloxacin Hydrochloride is indicated in adult patients for the treatment of Acute Bacterial Exacerbation of Chronic Bronchitis (ABECB) caused by susceptible isolates of Streptococcus pneumoniae, Haemophilus influenzae, Haemophilus parainfluenzae, Klebsiella pneumoniae, methicillin-susceptible Staphylococcus aureus, or Moraxella catarrhalis [see Clinical Studies (14.2)].

Because fluoroquinolones, including Moxifloxacin Hydrochloride, have been associated with serious adverse reactions [see Warnings and Precautions (5.1-5.13)] and for some patients ABECB is self-limiting, reserve Moxifloxacin Hydrochloride for treatment of ABECB in patients who have no alternative treatment options.

1.8 Usage

To reduce the development of drug-resistant bacteria and maintain the effectiveness of Moxifloxacin Hydrochloride and other antibacterial drugs, Moxifloxacin Hydrochloride should be used only to treat or prevent infections that are proven or strongly suspected to be caused by susceptible bacteria. When culture and susceptibility information are available, they should be considered in selecting or modifying antibacterial therapy. In the absence of such data, local epidemiology and susceptibility patterns may contribute to the empiric selection of therapy.

2 DOSAGE AND ADMINISTRATION

2.1 Dosage in Adult Patients

The dose of Moxifloxacin Hydrochloride is 400 mg (orally or as an intravenous infusion) once every 24 hours. The duration of therapy depends on the type of infection as described in Table 1.

Table 1: Dosage and Duration of Therapy in Adult Patients

Type of Infectiona

Dose
Every 24 hours

Durationb
(days)

Community Acquired Pneumonia (1.1)

400 mg

7–14

Uncomplicated Skin and Skin Structure Infections (SSSI) (1.2)

400 mg

7

Complicated SSSI (1.3)

400 mg

7–21

Complicated Intra-Abdominal Infections (1.4)

400 mg

5–14

Plague (1.5)C

400 mg

10–14

Acute Bacterial Sinusitis (ABS) (1.6)

400 mg

10

Acute Bacterial Exacerbation of Chronic Bronchitis (ABECB) (1.7)

400 mg

5

a)
Due to the designated pathogens [see Indications and Usage (1)].
b)
Sequential therapy (intravenous to oral) may be instituted at the discretion of the physician
c)
Drug administration should begin as soon as possible after suspected or confirmed exposure toYersinia pestis.

Conversion of Intravenous to Oral Dosing in Adults

Intravenous formulation is indicated when it offers a route of administration advantageous to the patient (for example, patient cannot tolerate an oral dosage form). When switching from intravenous to oral formulation, no dosage adjustment is necessary. Patients whose therapy is started with Moxifloxacin Hydrochloride Injection may be switched to Moxifloxacin Hydrochloride Tablets when clinically indicated at the discretion of the physician.

2.2 Important Administration Instructions

With Multivalent Cations

Administer Moxifloxacin Hydrochloride Tablets at least 4 hours before or 8 hours after products containing magnesium, aluminum, iron or zinc, including antacids, sucralfate, multivitamins and didanosine buffered tablets for oral suspension or the pediatric powder for oral solution [see Drug Interactions (7.1) and Clinical Pharmacology (12.3)].

With Food

Moxifloxacin Hydrochloride Tablets can be taken with or without food, drink fluids liberally.

3 DOSAGE FORMS AND STRENGTHS

Oblong, dull red, film-coated tablets imprinted with “BAYER” on one side and “M400” on the other containing moxifloxacin hydrochloride (equivalent to 400 mg moxifloxacin).

4 CONTRAINDICATIONS

Moxifloxacin Hydrochloride is contraindicated in persons with a history of hypersensitivity to moxifloxacin or any member of the quinolone class of antibacterials [see Warnings and Precautions

5 WARNINGS AND PRECAUTIONS

5.1 Disabling and Potentially Irreversible Serious Adverse Reactions Including Tendinitis and Tendon Rupture, Peripheral Neuropathy, and Central Nervous System Effects

Fluoroquinolones, including Moxifloxacin Hydrochloride, have been associated with disabling and potentially irreversible serious adverse reactions from different body systems that can occur together in the same patient. Commonly seen adverse reactions include tendinitis, tendon rupture, arthralgia, myalgia, peripheral neuropathy, and central nervous system effects (hallucinations, anxiety, depression, insomnia, severe headaches, and confusion). These reactions can occur within hours to weeks after starting Moxifloxacin Hydrochloride. Patients of any age or without pre-existing risk factors have experienced these adverse reactions [see Warnings and Precautions (5.2, 5.3, 5.4)].

Discontinue Moxifloxacin Hydrochloride immediately at the first signs or symptoms of any serious adverse reaction. In addition, avoid the use of fluoroquinolones, including Moxifloxacin Hydrochloride, in patients who have experienced any of these serious adverse reactions associated with fluoroquinolones.

5.2 Tendinitis and Tendon Rupture

Fluoroquinolones, including Moxifloxacin Hydrochloride, have been associated with an increased risk of tendinitis and tendon rupture in all ages [see Warnings and Precautions (5.1) and Adverse Reactions (6.2)]. This adverse reaction most frequently involves the Achilles tendon, and has also been reported with the rotator cuff (the shoulder), the hand, the biceps, the thumb, and other tendons. Tendinitis or tendon rupture can occur within hours or days of starting moxifloxacin or as long as several months after completion of therapy. Tendinitis and tendon rupture can occur bilaterally.

The risk of developing fluoroquinolone-associated tendinitis and tendon rupture is increased in patients over 60 years of age, in patients taking corticosteroid drugs, and in patients with kidney, heart or lung transplants. Other factors that may independently increase the risk of tendon rupture include strenuous physical activity, renal failure, and previous tendon disorders such as rheumatoid arthritis. Tendinitis and tendon rupture have also occurred in patients taking fluoroquinolones who do not have the above risk factors. Discontinue Moxifloxacin Hydrochloride immediately if the patient experiences pain, swelling, inflammation or rupture of a tendon. Patients should be advised to rest at the first sign of tendinitis or tendon rupture, and to contact their healthcare provider regarding changing to a non-quinolone antimicrobial drug. Avoid fluoroquinolones, including Moxifloxacin Hydrochloride, in patients who have a history of tendon disorders or who have experienced tendinitis or tendon rupture [see Adverse Reactions (6.2)].

5.3 Peripheral Neuropathy

Fluoroquinolones, including Moxifloxacin Hydrochloride, have been associated with an increased risk of peripheral neuropathy. Cases of sensory or sensorimotor axonal polyneuropathy affecting small and/or large axons resulting in paresthesias, hypoesthesias, dysesthesias and weakness have been reported in patients receiving fluoroquinolones including Moxifloxacin Hydrochloride. Symptoms may occur soon after initiation of Moxifloxacin Hydrochloride and may be irreversible in some patients [see Warnings and Precautions (5.1) and Adverse Reactions (6.1, 6.2)].

Discontinue Moxifloxacin Hydrochloride immediately if the patient experiences symptoms of peripheral neuropathy including pain, burning, tingling, numbness, and/or weakness or other alterations of sensation including light touch, pain, temperature, position sense, and vibratory sensation. Avoid fluoroquinolones, including Moxifloxacin Hydrochloride, in patients who have previously experienced peripheral neuropathy

5.4 Central Nervous System Effects

Fluoroquinolones, including Moxifloxacin Hydrochloride, have been associated with an increased risk of central nervous system (CNS) reactions, including: convulsions and increased intracranial pressure (including pseudotumor cerebri) and toxic psychosis, Fluoroquinolones may also cause CNS reactions of nervousness, agitation, insomnia, anxiety, nightmares, paranoia, dizziness, confusion, tremors, hallucinations, depression, and, suicidal thoughts or acts. These adverse reactions may occur following the first dose. If these reactions occur in patients receiving Moxifloxacin Hydrochloride, discontinue Moxifloxacin Hydrochloride immediately and institute appropriate measures. As with all fluoroquinolones, use Moxifloxacin Hydrochloride when the benefits of treatment exceed the risks in patients with known or suspected CNS disorders (for example, severe cerebral arteriosclerosis, epilepsy) or in the presence of other risk factors that may predispose to seizures or lower the seizure threshold [see Drug Interactions (7.4)].

5.5 Exacerbation of Myasthenia Gravis

Fluoroquinolones, including Moxifloxacin Hydrochloride, have neuromuscular blocking activity and may exacerbate muscle weakness in patients with myasthenia gravis. Postmarketing serious adverse reactions, including deaths and requirement for ventilatory support, have been associated with fluoroquinolone use in patients with myasthenia gravis. Avoid Moxifloxacin Hydrochloride in patients with known history of myasthenia gravis.

5.6 QT Prolongation

Moxifloxacin Hydrochloride has been shown to prolong the QT interval of the electrocardiogram in some patients. Following oral dosing with 400 mg of Moxifloxacin Hydrochloride the mean (± SD) change in QTc from the pre-dose value at the time of maximum drug concentration was 6 msec (± 26) (n = 787). Following a course of daily intravenous dosing (400 mg; 1 hour infusion each day) the mean change in QTc from the Day 1 pre-dose value was 10 msec (±22) on Day 1 (n=667) and 7 msec (± 24) on Day 3 (n = 667).

Avoid Moxifloxacin Hydrochloride in patients with the following risk factors due to the lack of clinical experience with the drug in these patient populations:

•
Known prolongation of the QT interval
•
Ventricular arrhythmias including torsade de pointes because QT prolongation may lead to an increased risk for these conditions
•
Ongoing proarrhythmic conditions, such as clinically significant bradycardia and acute myocardial ischemia,
•
Uncorrected hypokalemia or hypomagnesemia
•
Class IA (for example, quinidine, procainamide) or Class III (for example, amiodarone, sotalol) antiarrhythmic agents
•
Other drugs that prolong the QT interval such as cisapride, erythromycin, antipsychotics, and tricyclic antidepressants

Elderly patients using intravenous Moxifloxacin Hydrochloride may be more susceptible to drug-associated QT prolongation [see Use In Specific Populations (8.5)].

In patients with mild, moderate, or severe liver cirrhosis, metabolic disturbances associated with hepatic insufficiency may lead to QT prolongation. Monitor ECG in patients with liver cirrhosis treated with Moxifloxacin Hydrochloride [see Clinical Pharmacology (12.3)].

The magnitude of QT prolongation may increase with increasing concentrations of the drug or increasing rates of infusion of the intravenous formulation. Therefore the recommended dose or infusion rate should not be exceeded.

In premarketing clinical trials, the rate of cardiovascular adverse reactions was similar in 798 Moxifloxacin Hydrochloride and 702 comparator treated patients who received concomitant therapy with drugs known to prolong the QTc interval. No excess in cardiovascular morbidity or mortality attributable to QTc prolongation occurred with Moxifloxacin Hydrochloride treatment in over 15,500 patients in controlled clinical studies, including 759 patients who were hypokalemic at the start of treatment, and there was no increase in mortality in over 18,000 Moxifloxacin Hydrochloride tablet treated patients in a postmarketing observational study in which ECGs were not performed.

5.7 Other Serious and Sometimes Fatal Adverse Reactions

Other serious and sometimes fatal adverse reactions, some due to hypersensitivity, and some due to uncertain etiology, have been reported in patients receiving therapy with fluoroquinolones, including Moxifloxacin Hydrochloride. These reactions may be severe and generally occur following the administration of multiple doses. Clinical manifestations may include one or more of the following:

•
Fever, rash, or severe dermatologic reactions (for example, toxic epidermal necrolysis, Stevens-Johnson syndrome)
•
Vasculitis; arthralgia; myalgia; serum sickness
•
Allergic pneumonitis
•
Interstitial nephritis; acute renal insufficiency or failure
•
Hepatitis; jaundice; acute hepatic necrosis or failure
•
Anemia, including hemolytic and aplastic; thrombocytopenia, including thrombotic thrombocytopenic purpura; leukopenia; agranulocytosis; pancytopenia; and/or other hematologic abnormalities

Discontinue Moxifloxacin Hydrochloride immediately at the first appearance of a skin rash, jaundice, or any other sign of hypersensitivity and institute supportive measures.

5.8 Hypersensitivity Reactions

Serious anaphylactic reactions, some following the first dose, have been reported in patients receiving fluoroquinolone therapy, including Moxifloxacin Hydrochloride. Some reactions were accompanied by cardiovascular collapse, loss of consciousness, tingling, pharyngeal or facial edema, dyspnea, urticaria, and itching. Discontinue Moxifloxacin Hydrochloride at the first appearance of a skin rash or any other sign of hypersensitivity [see Warnings and Precautions (5.7)].

5.9 Clostridium difficile-Associated Diarrhea

Clostridium difficile-associated diarrhea (CDAD) has been reported with use of nearly all antibacterial agents, including Moxifloxacin Hydrochloride, and may range in severity from mild diarrhea to fatal colitis. Treatment with antibacterial agents alters the normal flora of the colon leading to overgrowth of C. difficile.

C. difficile produces toxins A and B which contribute to the development of CDAD. Hypertoxin producing strains of C. difficile cause increased morbidity and mortality, as these infections can be refractory to antimicrobial therapy and may require colectomy. CDAD must be considered in all patients who present with diarrhea following antibacterial use. Careful medical history is necessary since CDAD has been reported to occur over two months after the administration of antibacterial agents.

If CDAD is suspected or confirmed, ongoing antibiotic use not directed against C. difficile may need to be discontinued. Appropriate fluid and electrolyte management, protein supplementation, antibiotic treatment of C. difficile, and surgical evaluation should be instituted as clinically indicated.

5.10 Arthropathic Effects in Animals

In immature dogs, oral administration of Moxifloxacin Hydrochloride caused lameness. Histopathological examination of the weight-bearing joints of these dogs revealed permanent lesions of the cartilage. Related quinolone-class drugs also produce erosions of cartilage of weight-bearing joints and other signs of arthropathy in immature animals of various species [see Nonclinical Toxicology (13.2)].

5.11 Blood Glucose Disturbances

As with all fluoroquinolones, disturbances in blood glucose, including both hypoglycemia and hyperglycemia have been reported with Moxifloxacin Hydrochloride. In Moxifloxacin Hydrochloride-treated patients, dysglycemia occurred predominantly in elderly diabetic patients receiving concomitant treatment with an oral hypoglycemic agent (for example, sulfonylurea) or with insulin. In diabetic patients, careful monitoring of blood glucose is recommended. If a hypoglycemic reaction occurs, Moxifloxacin Hydrochloride should be discontinued and appropriate therapy should be initiated immediately [see Drug Interactions (7.3)].

5.12 Photosensitivity/Phototoxicity

Moderate to severe photosensitivity/phototoxicity reactions, the latter of which may manifest as exaggerated sunburn reactions (for example, burning, erythema, exudation, vesicles, blistering, edema) involving areas exposed to light (typically the face, “V” area of the neck, extensor surfaces of the forearms, dorsa of the hands), can be associated with the use of fluoroquinolones, including Moxifloxacin Hydrochloride, after sun or UV light exposure. Therefore, excessive exposure to these sources of light should be avoided. Moxifloxacin Hydrochloride should be discontinued if phototoxicity occurs [see Clinical Pharmacology (12.2)].

5.13 Development of Drug Resistant Bacteria

Prescribing Moxifloxacin Hydrochloride in the absence of a proven or strongly suspected bacterial infection or a prophylactic indication is unlikely to provide benefit to the patient and increases the risk of the development of drug-resistant bacteria.

6 ADVERSE REACTIONS

The following serious and otherwise important adverse reactions are discussed in greater detail in the warnings and precautions section of the label:

•
Disabling and Potentially Irreversible Serious Adverse Reactions Including Tendinitis and Tendon Rupture, Peripheral Neuropathy, and Central Nervous System Effects [see Warnings and Precautions (5.1)]
•
Tendinitis and Tendon Rupture [see Warnings and Precautions (5.2)]
•
Peripheral Neuropathy [see Warnings and Precautions (5.3)]
•
Central Nervous System Effects [see Warnings and Precautions (5.4)]
•
Exacerbation of Myasthenia Gravis [see Warnings and Precautions (5.5)]
•
QT Prolongation [see Warnings and Precautions (5.6)]
•
Other Serious and Sometimes Fatal Adverse Reactions [see Warnings and Precautions (5.7)]
•
Hypersensitivity Reactions [see Warnings and Precautions (5.8)]
•
Clostridium difficile-Associated Diarrhea [see Warnings and Precautions (5.9)]
•
Blood Glucose Disturbances [see Warnings and Precautions (5.11)]
•
Photosensitivity/Phototoxicity [see Warnings and Precautions (5.12)]
•
Development of Drug Resistant Bacteria [see Warnings and Precautions (5.13)]

6.1 Clinical Trials Experience

Because clinical trials are conducted under widely varying conditions, adverse reaction rates observed in the clinical trials of a drug cannot be directly compared to rates in the clinical trials of another drug and may not reflect the rates observed in practice.

The data described below reflect exposure to Moxifloxacin Hydrochloride in 14981 patients in 71 active controlled Phase II–IV clinical trials in different indications [see Indications and Usage (1)]. The population studied had a mean age of 50 years (approximately 73% of the population was less than 65 years of age), 50% were male, 63% were Caucasian, 12% were Asian and 9% were Black. Patients received Moxifloxacin Hydrochloride 400 mg once daily oral, intravenous, or sequentially (intravenous followed by oral). Treatment duration was usually 6 to 10 days, and the mean number of days on therapy was 9 days.

Discontinuation of Moxifloxacin Hydrochloride due to adverse reactions occurred in 5% of patients overall, 4% of patients treated with 400 mg PO, 4% with 400 mg intravenous and 8% with sequential therapy 400 mg oral/intravenous. The most common adverse reactions (>0.3%) leading to discontinuation with the 400 mg oral doses were nausea, diarrhea, dizziness, and vomiting. The most common adverse reaction leading to discontinuation with the 400 mg intravenous dose was rash. The most common adverse reactions leading to discontinuation with the 400 mg intravenous/oral sequential dose were diarrhea, pyrexia.

Adverse reactions occurring in 1% of Moxifloxacin Hydrochloride-treated patients and less common adverse reactions, occurring in 0.1 to 1% of Moxifloxacin Hydrochloride-treated patients, are shown in Tables 2 and Table 3, respectively. The most common adverse drug reactions (3%) are nausea, diarrhea, headache, and dizziness.

Table 2: Common (1% or more) Adverse Reactions Reported in Active-Controlled Clinical Trials with Moxifloxacin Hydrochloride

System Organ Class

Adverse Reactions

%

(N=14,981)

Blood and Lymphatic System Disorders

Anemia

1

Gastrointestinal Disorders

Nausea

7

Diarrhea

6

Vomiting

2

Constipation

2

Abdominal pain

2

Dyspepsia

1

General Disorders and Administration Site Conditions

Pyrexia

1

Investigations

Alanine aminotransferase increased

1

Metabolism and Nutritional Disorder

Hypokalemia

1

Nervous System Disorders

Headache

4

Dizziness

3

Psychiatric Disorders

Insomnia

2

Table 3: Less Common (0.1 to less than 1%) Adverse Reactions Reported in Active-Controlled Clinical Trials with Moxifloxacin Hydrochloride (N=14,981)
System Organ Class Adverse Reactions

Blood and Lymphatic System Disorders

Thrombocythemia

Eosinophilia

Neutropenia

Thrombocytopenia

Leukopenia

Leukocytosis

Cardiac Disorders

Atrial fibrillation

Palpitations

Tachycardia

Angina pectoris

Cardiac failure

Cardiac arrest

Bradycardia

Ear and Labyrinth Disorders

Vertigo

Tinnitus

Eye Disorders

Vision blurred

Gastrointestinal Disorders

Dry mouth

Abdominal discomfort

Flatulence

Abdominal distention

Gastritis

Gastroesophageal reflux disease

General Disorders and Administration Site Conditions

Fatigue

Chest pain

Asthenia

Pain

Malaise

Infusion site extravasation

Edema

Chills

Chest discomfort

Facial pain

Hepatobiliary disorders

Hepatic function abnormal

Infections and Infestations

Candidiasis

Vaginal infection

Fungal infection

Gastroenteritis

Investigations

Aspartate aminotransferase increased

Gamma-glutamyltransferase increased

Blood alkaline phosphatase increased

Electrocardiogram QT prolonged

Blood lactate dehydrogenase increased

Blood amylase increased

Lipase increased

Blood creatinine increased

Blood urea increased

Hematocrit decreased

Prothrombin time prolonged

Eosinophil count increased

Activated partial thromboplastin time prolonged

Blood triglycerides increased

Blood uric acid increased

Metabolism and Nutrition Disorders

Hyperglycemia

Anorexia

Hyperlipidemia

Decreased appetite

Dehydration

Musculoskeletal and Connective Tissue Disorders

Back pain

Pain in extremity

Arthralgia

Muscle spasms

Musculoskeletal pain

Nervous System Disorders

Dysgeusia

Somnolence

Tremor

Lethargy

Paresthesia

Hypoesthesia

Syncope

Psychiatric Disorders

Anxiety

Confusional state

Agitation

Depression

Nervousness

Restlessness

Hallucination

Disorientation

Renal and Urinary Disorders

Renal failure

Dysuria

Reproductive System and Breast Disorders

Vulvovaginal pruritus

Respiratory, Thoracic, and Mediastinal Disorders

Dyspnea

Asthma

Wheezing

Bronchospasm

Skin and Subcutaneous Tissue Disorders

Rash

Pruritus

Hyperhidrosis

Erythema

Urticaria

Dermatitis allergic

Night sweats

Vascular Disorders

Hypertension

Hypotension

Phlebitis

Laboratory Changes

Changes in laboratory parameters, which are not listed above and which occurred in 2% or more of patients and at an incidence greater than in controls included: increases in mean corpuscular hemoglobin (MCH), neutrophils, white blood cells (WBCs), prothrombin time (PT) ratio, ionized calcium, chloride, albumin, globulin, bilirubin; decreases in hemoglobin, red blood cells (RBCs), neutrophils, eosinophils, basophils, glucose, oxygen partial pressure (pO2), bilirubin, and amylase. It cannot be determined if any of the above laboratory abnormalities were caused by the drug or the underlying condition being treated.

6.2 Postmarketing Experience

Table 4 below lists adverse reactions that have been identified during post-approval use of Moxifloxacin Hydrochloride. Because these reactions are reported voluntarily from a population of uncertain size, it is not always possible to reliably estimate their frequency or establish a causal relationship to drug exposure.

Table 4: Postmarketing Reports of Adverse Drug Reactions

System Organ Class

Adverse Reactions

Blood and Lymphatic System Disorders

Agranulocytosis

Pancytopenia

[see Warnings and Precautions (5.7)]

Cardiac Disorders

Ventricular tachyarrhythmias (including in very rare cases cardiac arrest and torsade de pointes, and usually in patients with concurrent severe underlying proarrhythmic conditions)

Ear and Labyrinth Disorders

Hearing impairment, including deafness(reversible in majority of cases)

Eye Disorders

Vision loss (especially in the course of CNS reactions, transient in majority of cases)

Hepatobiliary Disorders

Hepatitis (predominantly cholestatic)

Hepatic failure (including fatal cases)

Jaundice

Acute hepatic necrosis

[see Warnings and Precautions (5.7)]

Immune System Disorders

Anaphylactic reaction

Anaphylactic shock

Angioedema (including laryngeal edema)

[see Warnings and Precautions (5.7, 5.8)]

Musculoskeletal and Connective Tissue Disorders

Tendon rupture

[see Warnings and Precautions (5.2)]

Nervous System Disorders

Altered coordination

Abnormal gait

[see Warnings and Precautions (5.3)]

Myasthenia gravis (exacerbation of)

[see Warnings and Precautions (5.5)]

Muscle weakness

Peripheral neuropathy (that may be irreversible), polyneuropathy

[see Warnings and Precautions (5.3)]

Psychiatric Disorders

Psychotic reaction (very rarely culminating in self-injurious behavior, such as suicidal ideation/thoughts or suicide attempts [see Warnings and Precautions (5.4)]

Renal and Urinary Disorders

Interstitial nephritis

[see Warnings and Precautions (5.7)]

Respiratory, Thoracic and Mediastinal Disorders

Allergic pneumonitis

[see Warnings and Precautions (5.7)]

Skin and Subcutaneous Tissue Disorders

Photosensitivity/phototoxicity reaction

[see Warnings and Precautions (5.12)]

Stevens-Johnson syndrome

Toxic epidermal necrolysis

[see Warnings and Precautions (5.7)]

7 DRUG INTERACTIONS

7.1 Antacids, Sucralfate, Multivitamins and other Products Containing Multivalent Cations

Fluoroquinolones, including Moxifloxacin Hydrochloride, form chelates with alkaline earth and transition metal cations. Oral administration of Moxifloxacin Hydrochloride with antacids containing aluminum or magnesium, with sucralfate, with metal cations such as iron, or with multivitamins containing iron or zinc, or with formulations containing divalent and trivalent cations such as didanosine buffered tablets for oral suspension or the pediatric powder for oral solution, may substantially interfere with the absorption of Moxifloxacin Hydrochloride, resulting in systemic concentrations considerably lower than desired. Therefore, Moxifloxacin Hydrochloride should be taken at least 4 hours before or 8 hours after these agents [see Dosage and Administration (2.2) and Clinical Pharmacology (12.3)].

7.2 Warfarin

Fluoroquinolones, including Moxifloxacin Hydrochloride, have been reported to enhance the anticoagulant effects of warfarin or its derivatives in the patient population. In addition, infectious disease and its accompanying inflammatory process, age, and general status of the patient are risk factors for increased anticoagulant activity. Therefore the prothrombin time, International Normalized Ratio (INR), or other suitable anticoagulation tests should be closely monitored if Moxifloxacin Hydrochloride is administered concomitantly with warfarin or its derivatives [see Adverse Reactions (6.2) and Clinical Pharmacology (12.3)].

7.3 Antidiabetic Agents

Disturbances of blood glucose, including hyperglycemia and hypoglycemia, have been reported in patients treated concomitantly with fluoroquinolones, including Moxifloxacin Hydrochloride, and an antidiabetic agent. Therefore, careful monitoring of blood glucose is recommended when these agents are co-administered. If a hypoglycemic reaction occurs, Moxifloxacin Hydrochloride should be discontinued and appropriate therapy should be initiated immediately [see Warnings and Precautions (5.11) and Adverse Reactions (6.1)].

7.4 Nonsteroidal Anti-Inflammatory Drugs

The concomitant administration of a nonsteroidal anti-inflammatory drug (NSAID) with a fluoroquinolone, including Moxifloxacin Hydrochloride, may increase the risks of CNS stimulation and convulsions [see Warnings and Precautions (5.4)].

7.5 Drugs that Prolong QT

There is limited information available on the potential for a pharmacodynamic interaction in humans between Moxifloxacin Hydrochloride and other drugs that prolong the QTc interval of the electrocardiogram. Sotalol, a Class III antiarrhythmic, has been shown to further increase the QTc interval when combined with high doses of intravenous Moxifloxacin Hydrochloride in dogs. Therefore, Moxifloxacin Hydrochloride should be avoided with Class IA and Class III antiarrhythmics [see Warnings and Precautions, (5.6) and Nonclinical Toxicology (13.2)].

8 USE IN SPECIFIC POPULATIONS

8.1 Pregnancy

Risk Summary

There are no available human data establishing a drug associated risk with the use of moxifloxacin.

Based on animal studies with moxifloxacin, Moxifloxacin may cause fetal harm. Moxifloxacin was not teratogenic when administered to pregnant rats (IV and oral), rabbits (IV), and monkeys (oral) at exposures that were 0.25–2.5 times of those at the human clinical dose (400 mg/day Moxifloxacin). However, when Moxifloxacin was administered to rats and rabbits during pregnancy and throughout lactation (rats only) at doses associated with maternal toxicity, decreased neonatal body weights, increased incidence of skeletal variations (rib and vertebra combined), and increased fetal loss were observed (see Data). Advise pregnant women of the potential risk to the fetus.

The background risk of major birth defects and miscarriage for the indicated population is unknown. However, the background risk in the U.S. general population of major birth defects is 2 to 4% and of miscarriage is 15 to 20% of clinically recognized pregnancies.

Data

Animal Data

Animal reproductive and development studies were done in rats, rabbits and cynomolgus macaques. Moxifloxacin was not teratogenic when administered to pregnant rats during organogenesis (gestation days 6 to 17) at oral doses as high as 500 mg/kg/day or 0.24 times the maximum recommended human dose based on systemic exposure (AUC), but decreased fetal body weights and slightly delayed fetal skeletal development were observed. Intravenous administration of 80 mg/kg/day (approximately 2 times the maximum recommended human dose based on body surface area) to pregnant rats resulted in maternal toxicity and a marginal effect on fetal and placental weights and the appearance of the placenta (Gestation days 6 to 17). There was no evidence of teratogenicity at intravenous doses as high as 80 mg/kg/day (approximately 2 times the maximum recommended human dose based on body surface area) in pregnant rats during organogenesis (Gestation days 6 to 17). Intravenous administration of 20 mg/kg/day (approximately equal to the maximum recommended human oral dose based upon systemic exposure) to pregnant rabbits during organogenesis (gestation days 6 to 20) resulted in decreased fetal body weights and delayed fetal skeletal ossification. When rib and vertebral malformations were combined, there was an increased fetal and litter incidence of these effects in rabbits. Signs of maternal toxicity in rabbits at this dose included mortality, abortions, marked reduction of food consumption, decreased water intake, body weight loss and hypoactivity. There was no evidence of teratogenicity when pregnant cynomolgus macaques were given oral doses as high as 100 mg/kg/day (2.5 times the maximum recommended human dose based upon systemic exposure) during organogenesis (gestation days 20 to 50). An increased incidence of smaller fetuses was observed at 100 mg/kg/day in macaques. In a pre- and postnatal development study conducted in rats given oral doses from Gestation day 6, throughout gestation and rearing to Postpartum day 21, effects observed at 500 mg/kg/day (0.24 times the maximum recommended human dose based on systemic exposure (AUC)) included slight increases in duration of pregnancy and prenatal loss, reduced pup birth weight and decreased neonatal survival. Treatment-related maternal mortality occurred during gestation at 500 mg/kg/day in this study.

8.2 Lactation

Risk Summary

It is not known if Moxifloxacin is present in human milk. Based on animal studies in rats, Moxifloxacin may be excreted in human milk (see Data).

The developmental and health benefits of breastfeeding should be considered along with the mother’s clinical need for Moxifloxacin and any potential adverse effects on the breastfed child from Moxifloxacin or from the underlying maternal condition.

Data

In lactating rats given a single oral dose of 4.59 mg/kg moxifloxacin (approximately 9 times less than the recommended human dose based on body surface area) 8 days postpartum, there was very low excretion of substance-related radioactivity into the milk, amounting to approximately 0.03% of the dose.

8.4 Pediatric Use

Effectiveness in pediatric patients and adolescents less than 18 years of age has not been established. Moxifloxacin causes arthropathy in juvenile animals. Limited information on the safety of Moxifloxacin in 301 pediatric patients is available from the cIAI trial [see BOXED WARNING, Warnings and Precautions (5.9) and Nonclinical Toxicology (13.2)].

Active Controlled Trial in Complicated Intra-Abdominal Infection (cIAI)

The safety and efficacy of Moxifloxacin in pediatric patients for the treatment of cIAI has not been demonstrated.

Pediatric patients 3 months to <18 years of age (mean age of 12 ± 4 years) were enrolled in a single randomized, double-blind, active controlled trial in cIAI including appendicitis with perforation, abscesses and peritonitis.

Pediatric patients were randomized (2:1) to receive either Moxifloxacin or comparator. This study enrolled 451 patients who received study medication, 301 treated with moxifloxacin, and 150 with comparator. Of the 301 pediatric patients treated with Moxifloxacin, 15 were below the age of 6 years and 286 were between the ages of 6–<18 years.

Patients received sequential intravenous/oral Moxifloxacin or comparator (intravenous ertapenem followed by oral amoxicillin/clavulanate) for 5 to 14 days (mean duration was 9 days with a range of 1 to 24 days).

The overall adverse reaction profile in pediatric patients was comparable to that of adult patients. The most frequently occurring adverse reactions in pediatric patients treated with Moxifloxacin were QT prolongation 9.3% (28/301), vomiting, 6.6% (20/301) diarrhea 3.7% (11/301), arthralgia 3.0% (9/301), and phlebitis 2.7% (8/301) (see Table 5). Discontinuation of study drug due to an adverse reaction was reported in 5.3% (16/301) of Moxifloxacin-treated patients versus 1.3% (2/150) of comparator-treated patients. The adverse reaction profile of Moxifloxacin or comparator was similar across all age groups studied.

Musculoskeletal adverse reactions were monitored and followed up to 5 years after the end of study treatment. The rates of musculoskeletal adverse reactions were 4.3% (13/301) in the Moxifloxacin-treated group versus 3.3% (5/150) in the comparator-treated group. The majority of musculoskeletal adverse reactions were reported between 12 and 53 weeks after start of study treatment with complete resolution at the end of the study [see Warnings and Precautions (5.9) and Nonclinical Toxicology (13.2)].

Table 5 Incidence (%) of Selected Adverse Reactions in ≥2.0% of Pediatric Patients Treated with Moxifloxacin in cIAI Clinical Trial

System Organ Class Adverse Reactions Moxifloxacin
N = 301 (%) Comparator
N = 150 (%)
Gastrointestinal disorders Abdominal pain 8 (2.7) 3 (2.0)
Diarrhea 11 (3.7) 1 (0.7)
Vomiting 20 (6.6) 12 (8.0)
General disorders and administration site conditions Pyrexia 6 (2.0) 4 (2.7)

Investigations

Aspartate aminotransferase increased

2 (0.7)

3 (2.0)

Electrocardiogram QT prolonged

28 (9.3)

4 (2.7)

Musculoskeletal and connective tissue disorders

Arthralgia

9 (3.0)

2 (1.3)

Nervous system disorders

Headache

6 (2.0)

2 (1.3)

Vascular disorders

Phlebitis

8 (2.7)

0 (0)

Clinical response was assessed at the test-of-cure visit (28 to 42 days after end of treatment). The clinical response rates observed in the modified intent to treat population were 83.9% (208/248) for Moxifloxacin and 95.5% (127/133) for comparator; see Table 6.

Table 6: Clinical Response Rates at 28–42 Days After End of Treatment in Pediatric Patients with cIAI

Moxifloxacin n (%)

Comparator

n (%)

Difference2

(95% CI)

mITT Population1

N=248

N=133

Cure

208 (83.9)

127 (95.5)

-12.2 (-17.9, -6.4)

Failure

17 (6.9)

3 (2.3)

Indeterminate

21 (8.5)

3 (2.3)

Missing

2 (0.8)

0

1The modified intent-to-treat (mITT) population is defined as all subjects who were treated with at least one dose of study medication and who have at least one pre-treatment causative organism from the intra-abdominal site of infection or from blood cultures.

2Difference in clinical cure rates (Moxifloxacin - Comparator) and 95% confidence intervals, presented as percentages, are based on stratified analysis by age group using Mantel-Haenszel methods.

8.5 Geriatric Use

Geriatric patients are at increased risk for developing severe tendon disorders including tendon rupture when being treated with a fluoroquinolone such as Moxifloxacin Hydrochloride. This risk is further increased in patients receiving concomitant corticosteroid therapy. Tendinitis or tendon rupture can involve the Achilles, hand, shoulder, or other tendon sites and can occur during or after completion of therapy; cases occurring up to several months after fluoroquinolone treatment have been reported. Caution should be used when prescribing Moxifloxacin Hydrochloride to elderly patients especially those on corticosteroids. Patients should be informed of this potential side effect and advised to discontinue Moxifloxacin Hydrochloride and contact their healthcare provider if any symptoms of tendinitis or tendon rupture occur [see BOXED WARNING, and Warnings and Precautions (5.2)].

In controlled multiple-dose clinical trials, 23% of patients receiving oral Moxifloxacin Hydrochloride were greater than or equal to 65 years of age and 9% were greater than or equal to 75 years of age. The clinical trial data demonstrate that there is no difference in the safety and efficacy of oral Moxifloxacin Hydrochloride in patients aged 65 or older compared to younger adults.

In trials of intravenous use, 42% of Moxifloxacin Hydrochloride patients were greater than or equal to 65 years of age, and 23% were greater than or equal to 75 years of age. The clinical trial data demonstrate that the safety of intravenous Moxifloxacin Hydrochloride in patients aged 65 or older was similar to that of comparator-treated patients. In general, elderly patients may be more susceptible to drug-associated effects of the QT interval. Therefore, Moxifloxacin Hydrochloride should be avoided in patients taking drugs that can result in prolongation of the QT interval (for example, class IA or class III antiarrhythmics) or in patients with risk factors for torsade de pointes (for example, known QT prolongation, uncorrected hypokalemia) [see Warnings and Precautions (5.6), Drug Interactions (7.5), and Clinical Pharmacology (12.3)].

8.6 Renal Impairment

The pharmacokinetic parameters of moxifloxacin are not significantly altered in mild, moderate, severe, or end-stage renal disease. No dosage adjustment is necessary in patients with renal impairment, including those patients requiring hemodialysis (HD) or continuous ambulatory peritoneal dialysis (CAPD) [see Dosage and Administration (2), and Clinical Pharmacology (12.3)].

8.7 Hepatic Impairment

No dosage adjustment is recommended for mild, moderate, or severe hepatic insufficiency (Child-Pugh Classes A, B, or C). However, due to metabolic disturbances associated with hepatic insufficiency, which may lead to QT prolongation, Moxifloxacin Hydrochloride should be used with caution in these patients [see Warnings and Precaution (5.6) and Clinical Pharmacology, (12.3)].

10 OVERDOSAGE

Single oral overdoses up to 2.8 g were not associated with any serious adverse events. In the event of acute overdose, Empty the stomach and maintain adequate hydration. Monitor ECG due to the possibility of QT interval prolongation. Carefully observe the patient and give supportive treatment. The administration of activated charcoal as soon as possible after oral overdose may prevent excessive increase of systemic moxifloxacin exposure. About 3% and 9% of the dose of moxifloxacin, as well as about 2% and 4.5% of its glucuronide metabolite are removed by continuous ambulatory peritoneal dialysis and hemodialysis, respectively.

11 DESCRIPTION

Moxifloxacin Hydrochloride (moxifloxacin hydrochloride) is a synthetic antibacterial agent for oral and intravenous administration. Moxifloxacin, a fluoroquinolone, is available as the monohydrochloride salt of 1-cyclopropyl-7-[(S,S)-2,8-diazabicyclo[4.3.0]non-8-yl]-6-fluoro-8-methoxy-1,4-dihydro-4-oxo-3 quinoline carboxylic acid. It is a slightly yellow to yellow crystalline substance with a molecular weight of 437.9. Its empirical formula is C21H24FN3O4HCl and its chemical structure is as follows:

[Chem Struc]

•
Moxifloxacin Hydrochloride Tablets are available as film-coated tablets containing moxifloxacin hydrochloride (equivalent to 400 mg moxifloxacin).
•
The inactive ingredients are microcrystalline cellulose, lactose monohydrate, croscarmellose sodium, magnesium stearate, hypromellose, titanium dioxide, polyethylene glycol and ferric oxide.

12 CLINICAL PHARMACOLOGY

12.1 Mechanism of Action

Moxifloxacin Hydrochloride is a member of the fluoroquinolone class of antibacterial agents [see Microbiology (12.4)].

12.2 Pharmacodynamics

Photosensitivity Potential

A study of the skin response to ultraviolet (UVA and UVB) and visible radiation conducted in 32 healthy volunteers (8 per group) demonstrated that Moxifloxacin Hydrochloride does not show phototoxicity in comparison to placebo. The minimum erythematous dose (MED) was measured before and after treatment with Moxifloxacin Hydrochloride (200 mg or 400 mg once daily), lomefloxacin (400 mg once daily), or placebo. In this study, the MED measured for both doses of Moxifloxacin Hydrochloride were not significantly different from placebo, while lomefloxacin significantly lowered the MED [see Warnings and Precautions (5.12)].

12.3 Pharmacokinetics

Absorption

Moxifloxacin, given as an oral tablet, is well absorbed from the gastrointestinal tract. The absolute bioavailability of moxifloxacin is approximately 90 percent. Co-administration with a high fat meal (that is, 500 calories from fat) does not affect the absorption of moxifloxacin.

Consumption of 1 cup of yogurt with moxifloxacin does not affect the rate or extent of the systemic absorption (that is, area under the plasma concentration time curve (AUC).

Table 7: Mean (± SD) Cmax and AUC values following single and multiple doses of 400 mg moxifloxacin given orally

Cmax
(mg/L) AUC
(mg•h/L) Half-life
(hr)

Single Dose Oral
Healthy (n = 372)

3.1 ± 1

36.1 ± 9.1

11.5–15.6a

Multiple Dose Oral

Healthy young male/female (n = 15)

4.5 ± 0.5

48 ± 2.7

12.7 ± 1.9

Healthy elderly male (n = 8)

3.8 ± 0.3

51.8 ± 6.7

Healthy elderly female (n = 8)

4.6 ± 0.6

54.6 ± 6.7

Healthy young male (n = 8)

3.6 ± 0.5

48.2 ± 9

Healthy young female (n = 9)

4.2 ± 0.5

49.3 ± 9.5

a)
Range of means from different studies

Table 8: Mean (± SD) Cmax and AUC values following single and multiple doses of 400 mg moxifloxacin given by 1-hour intravenous infusion

Cmax
(mg/L) AUC
(mg•h/L) Half-life
(hour)

Single Dose intravenous

Healthy young male/female (n = 56)

3.9 ± 0.9

39.3 ± 8.6

8.2–15.4a

Patients (n = 118)

Male (n = 64)

4.4 ± 3.7

Female (n = 54)

4.5 ± 2

< 65 years (n = 58)

4.6 ± 4.2

≥ 65 years (n = 60)

4.3 ± 1.3

Multiple Dose intravenous

Healthy young male (n = 8)

4.2 ± 0.8

38 ± 4.7

14.8 ± 2.2

Healthy elderly (n =12; 8 male, 4 female)

6.1 ± 1.3

48.2 ± 0.9

10.1 ± 1.6

Patientsb (n = 107)

Male (n = 58)

4.2 ± 2.6

Female (n = 49)

4.6 ± 1.5

<65 years (n = 52)

4.1 ± 1.4

≥65 years (n = 55)

4.7 ± 2.7

a)
Range of means from different studies
b)
Expected C max (concentration obtained around the time of the end of the infusion)

Plasma concentrations increase proportionately with dose up to the highest dose tested (1200 mg single oral dose). The mean (± SD) elimination half-life from plasma is 12 ± 1.3 hours; steady-state is achieved after at least three days with a 400 mg once daily regimen.

Mean Steady-State Plasma Concentrations of Moxifloxacin Obtained With Once Daily Dosing of 400 mg
Either Orally (n=10) or by Intravenous Infusion (n=12)

[Plasma Figure]

Distribution

Moxifloxacin is approximately 30–50% bound to serum proteins, independent of drug concentration. The volume of distribution of moxifloxacin ranges from 1.7 to 2.7 L/kg. Moxifloxacin is widely distributed throughout the body, with tissue concentrations often exceeding plasma concentrations. Moxifloxacin has been detected in the saliva, nasal and bronchial secretions, mucosa of the sinuses, skin blister fluid, subcutaneous tissue, skeletal muscle, and abdominal tissues and fluids following oral or intravenous administration of 400 mg. Moxifloxacin concentrations measured post-dose in various tissues and fluids following a 400 mg oral or intravenous dose are summarized in Table 9. The rates of elimination of moxifloxacin from tissues generally parallel the elimination from plasma.

Table 9: Moxifloxacin Concentrations (mean ± SD) in Tissues and the Corresponding Plasma Concentrations After a Single 400 mg Oral or Intravenous Dosea

Tissue or Fluid N Plasma
Concentration
(mcg/mL) Tissue or Fluid
Concentration
(mcg/mL or mcg/g) Tissue
Plasma
Ratio

Respiratory

Alveolar Macrophages

5

3.3 ± 0.7

61.8 ± 27.3

21.2 ± 10

Bronchial Mucosa

8

3.3 ± 0.7

5.5 ± 1.3

1.7 ± 0.3

Epithelial Lining Fluid

5

3.3 ± 0.7

24.4 ± 14.7

8.7 ± 6.1

Sinus

Maxillary Sinus Mucosa

4

3.7 ± 1.1b

7.6 ± 1.7

2 ± 0.3

Anterior Ethmoid Mucosa

3

3.7 ± 1.1b

8.8 ± 4.3

2.2 ± 0.6

Nasal Polyps

4

3.7 ± 1.1b

9.8 ± 4.5

2.6 ± 0.6

Skin, Musculoskeletal

Blister Fluid

5

3 ± 0.5c

2.6 ± 0.9

0.9 ± 0.2

Subcutaneous Tissue

6

2.3 ± 0.4d

0.9 ± 0.3e

0.4 ± 0.6

Skeletal Muscle

6

2.3 ± 0.4d

0.9 ± 0.2e

0.4 ± 0.1

Intra-Abdominal

Abdominal tissue

8

2.9 ± 0.5

7.6 ± 2

2.7 ± 0.8

Abdominal exudate

10

2.3 ± 0.5

3.5 ±1.2

1.6 ± 0.7

Abscess fluid

6

2.7 ± 0.7

2.3 ±1.5

0.8 ± 0.4

a)
All moxifloxacin concentrations were measured 3 hours after a single 400 mg dose, except the abdominal tissue and exudate concentrations which were measured at 2 hours post-dose and the sinus concentrations which were measured 3 hours post-dose after 5 days of dosing.
b)
N = 5
c)
N = 7
d)
N = 12
e)
Reflects only non-protein bound concentrations of drug.

Metabolism

Approximately 52% of an oral or intravenous dose of moxifloxacin is metabolized via glucuronide and sulfate conjugation. The cytochrome P450 system is not involved in moxifloxacin metabolism, and is not affected by moxifloxacin. The sulfate conjugate (M1) accounts for approximately 38% of the dose, and is eliminated primarily in the feces. Approximately 14% of an oral or intravenous dose is converted to a glucuronide conjugate (M2), which is excreted exclusively in the urine. Peak plasma concentrations of M2 are approximately 40% those of the parent drug, while plasma concentrations of M1 are generally less than 10% those of moxifloxacin.

In vitro studies with cytochrome (CYP) P450 enzymes indicate that moxifloxacin does not inhibit CYP3A4, CYP2D6, CYP2C9, CYP2C19, or CYP1A2.

Excretion

Approximately 45% of an oral or intravenous dose of moxifloxacin is excreted as unchanged drug (~20% in urine and ~25% in feces). A total of 96% ± 4% of an oral dose is excreted as either unchanged drug or known metabolites. The mean (± SD) apparent total body clearance and renal clearance are 12 ± 2 L/hr and 2.6 ± 0.5 L/hr, respectively.

Pharmacokinetics in Specific Populations

Geriatric

Following oral administration of 400 mg moxifloxacin for 10 days in 16 elderly (8 male; 8 female) and 17 young (8 male; 9 female) healthy volunteers, there were no age-related changes in moxifloxacin pharmacokinetics. In 16 healthy male volunteers (8 young; 8 elderly) given a single 200 mg dose of oral moxifloxacin, the extent of systemic exposure (AUC and Cmax) was not statistically different between young and elderly males and elimination half-life was unchanged. No dosage adjustment is necessary based on age. In large phase III studies, the concentrations around the time of the end of the infusion in elderly patients following intravenous infusion of 400 mg were similar to those observed in young patients [see Use in Specific Populations (8.5)].

Gender

Following oral administration of 400 mg moxifloxacin daily for 10 days to 23 healthy males (19–75 years) and 24 healthy females (19–70 years), the mean AUC and Cmax were 8% and 16% higher, respectively, in females compared to males. There are no significant differences in moxifloxacin pharmacokinetics between male and female subjects when differences in body weight are taken into consideration.

A 400 mg single dose study was conducted in 18 young males and females. The comparison of moxifloxacin pharmacokinetics in this study (9 young females and 9 young males) showed no differences in AUC or Cmax due to gender. Dosage adjustments based on gender are not necessary.

Race

Steady-state moxifloxacin pharmacokinetics in male Japanese subjects were similar to those determined in Caucasians, with a mean Cmax of 4.1 mcg/mL, an AUC24 of 47 mcg•h/mL, and an elimination half-life of 14 hours, following 400 mg p.o. daily.

Renal Insufficiency

The pharmacokinetic parameters of moxifloxacin are not significantly altered in mild, moderate, severe, or end-stage renal disease. No dosage adjustment is necessary in patients with renal impairment, including those patients requiring hemodialysis (HD) or continuous ambulatory peritoneal dialysis (CAPD).

In a single oral dose study of 24 patients with varying degrees of renal function from normal to severely impaired, the mean peak concentrations (Cmax) of moxifloxacin were reduced by 21% and 28% in the patients with moderate (CLCR≥ 30 and ≤ 60 mL/min) and severe (CLCR<30 mL/min) renal impairment, respectively. The mean systemic exposure (AUC) in these patients was increased by 13%. In the moderate and severe renally impaired patients, the mean AUC for the sulfate conjugate (M1) increased by 1.7-fold (ranging up to 2.8-fold) and mean AUC and Cmax for the glucuronide conjugate (M2) increased by 2.8-fold (ranging up to 4.8-fold) and 1.4-fold (ranging up to 2.5-fold), respectively [see Use in Specific Populations (8.6)].

The pharmacokinetics of single dose and multiple dose moxifloxacin were studied in patients with CLCR< 20 mL/min on either hemodialysis or continuous ambulatory peritoneal dialysis (8 HD, 8 CAPD). Following a single 400 mg oral dose, the AUC of moxifloxacin in these HD and CAPD patients did not vary significantly from the AUC generally found in healthy volunteers. Cmax values of moxifloxacin were reduced by about 45% and 33% in HD and CAPD patients, respectively, compared to healthy, historical controls. The exposure (AUC) to the sulfate conjugate (M1) increased by 1.4- to 1.5-fold in these patients. The mean AUC of the glucuronide conjugate (M2) increased by a factor of 7.5, whereas the mean Cmax values of the glucuronide conjugate (M2) increased by a factor of 2.5 to 3, compared to healthy subjects. The sulfate and the glucuronide conjugates of moxifloxacin are not microbiologically active, and the clinical implication of increased exposure to these metabolites in patients with renal disease including those undergoing HD and CAPD has not been studied.

Oral administration of 400 mg QD Moxifloxacin Hydrochloride for 7 days to patients on HD or CAPD produced mean systemic exposure (AUCss) to moxifloxacin similar to that generally seen in healthy volunteers. Steady-state Cmax values were about 22% lower in HD patients but were comparable between CAPD patients and healthy volunteers. Both HD and CAPD removed only small amounts of moxifloxacin from the body (approximately 9% by HD, and 3% by CAPD). HD and CAPD also removed about 4% and 2% of the glucuronide metabolite (M2), respectively.

Hepatic Insufficiency

No dosage adjustment is recommended for mild, moderate, or severe hepatic insufficiency (Child-Pugh Classes A, B, or C). However, due to metabolic disturbances associated with hepatic insufficiency, which may lead to QT prolongation, Moxifloxacin Hydrochloride should be used with caution in these patients [see Warnings and Precautions (5.6) and Use in Specific Populations (8.7)].

In 400 mg single oral dose studies in 6 patients with mild (Child-Pugh Class A) and 10 patients with moderate (Child-Pugh Class B) hepatic insufficiency, moxifloxacin mean systemic exposure (AUC) was 78% and 102%, respectively, of 18 healthy controls and mean peak concentration (Cmax) was 79% and 84% of controls.

The mean AUC of the sulfate conjugate of moxifloxacin (M1) increased by 3.9-fold (ranging up to 5.9-fold) and 5.7-fold (ranging up to 8-fold) in the mild and moderate groups, respectively. The mean Cmaxof M1 increased by approximately 3-fold in both groups (ranging up to 4.7- and 3.9-fold). The mean AUC of the glucuronide conjugate of moxifloxacin (M2) increased by 1.5-fold (ranging up to 2.5-fold) in both groups. The mean Cmax of M2 increased by 1.6- and 1.3-fold (ranging up to 2.7- and 2.1-fold), respectively. The clinical significance of increased exposure to the sulfate and glucuronide conjugates has not been studied. In a subset of patients participating in a clinical trial, the plasma concentrations of moxifloxacin and metabolites determined approximately at the moxifloxacin Tmax following the first intravenous or oral Moxifloxacin Hydrochloride dose in the Child-Pugh Class C patients (n=10) were similar to those in the Child-Pugh Class A/B patients (n=5), and also similar to those observed in healthy volunteer studies.

Drug-Drug Interactions

The following drug interactions were studied in healthy volunteers or patients.

Antacids and iron significantly reduced bioavailability of moxifloxacin, as observed with other fluoroquinolones [see Drug Interactions (7.1)].

Calcium, digoxin, itraconazole, morphine, probenecid, ranitidine, theophylline, cyclosporine and warfarin did not significantly affect the pharmacokinetics of moxifloxacin. These results and the data from in vitro studies suggest that moxifloxacin is unlikely to significantly alter the metabolic clearance of drugs metabolized by CYP3A4, CYP2D6, CYP2C9, CYP2C19, or CYP1A2 enzymes.

Moxifloxacin had no clinically significant effect on the pharmacokinetics of atenolol, digoxin, glyburide, itraconazole, oral contraceptives, theophylline, cyclosporine and warfarin. However, fluoroquinolones, including Moxifloxacin Hydrochloride, have been reported to enhance the anticoagulant effects of warfarin or its derivatives in the patient population [see Drug Interactions (7.2)].

Antacids

When moxifloxacin (single 400 mg tablet dose) was administered two hours before, concomitantly, or 4 hours after an aluminum/magnesium-containing antacid (900 mg aluminum hydroxide and 600 mg magnesium hydroxide as a single oral dose) to 12 healthy volunteers there was a 26%, 60% and 23% reduction in the mean AUC of moxifloxacin, respectively. Moxifloxacin should be taken at least 4 hours before or 8 hours after antacids containing magnesium or aluminum, as well as sucralfate, metal cations such as iron, and multivitamin preparations with zinc, or didanosine buffered tablets for oral suspension or the pediatric powder for oral solution [see Dosage and Administration (2.2) and Drug Interactions (7.1)].

Atenolol

In a crossover study involving 24 healthy volunteers (12 male; 12 female), the mean atenolol AUC following a single oral dose of 50 mg atenolol with placebo was similar to that observed when atenolol was given concomitantly with a single 400 mg oral dose of moxifloxacin. The mean Cmax of single dose atenolol decreased by about 10% following co-administration with a single dose of moxifloxacin.

Calcium

Twelve healthy volunteers were administered concomitant moxifloxacin (single 400 mg dose) and calcium (single dose of 500 mg Ca++ dietary supplement) followed by an additional two doses of calcium 12 and 24 hours after moxifloxacin administration. Calcium had no significant effect on the mean AUC of moxifloxacin. The mean Cmax was slightly reduced and the time to maximum plasma concentration was prolonged when moxifloxacin was given with calcium compared to when moxifloxacin was given alone (2.5 hours versus 0.9 hours). These differences are not considered to be clinically significant.

Digoxin

No significant effect of moxifloxacin (400 mg once daily for two days) on digoxin (0.6 mg as a single dose) AUC was detected in a study involving 12 healthy volunteers. The mean digoxin Cmax increased by about 50% during the distribution phase of digoxin. This transient increase in digoxin Cmax is not viewed to be clinically significant. Moxifloxacin pharmacokinetics were similar in the presence or absence of digoxin. No dosage adjustment for moxifloxacin or digoxin is required when these drugs are administered concomitantly.

Glyburide

In diabetics, glyburide (2.5 mg once daily for two weeks pretreatment and for five days concurrently) mean AUC and Cmax were 12% and 21% lower, respectively, when taken with moxifloxacin (400 mg once daily for five days) in comparison to placebo. Nonetheless, blood glucose levels were decreased slightly in patients taking glyburide and moxifloxacin in comparison to those taking glyburide alone, suggesting no interference by moxifloxacin on the activity of glyburide. These interaction results are not viewed as clinically significant.

Iron

When moxifloxacin tablets were administered concomitantly with iron (ferrous sulfate 100 mg once daily for two days), the mean AUC and Cmax of moxifloxacin was reduced by 39% and 59%, respectively. Moxifloxacin should only be taken more than 4 hours before or 8 hours after iron products [see Dosage and Administration (2.2) and Drug Interactions (7.1)].

Itraconazole

In a study involving 11 healthy volunteers, there was no significant effect of itraconazole (200 mg once daily for 9 days), a potent inhibitor of cytochrome P4503A4, on the pharmacokinetics of moxifloxacin (a single 400 mg dose given on the 7th day of itraconazole dosing). In addition, moxifloxacin was shown not to affect the pharmacokinetics of itraconazole.

Morphine

No significant effect of morphine sulfate (a single 10 mg intramuscular dose) on the mean AUC and Cmax of moxifloxacin (400 mg single dose) was observed in a study of 20 healthy male and female volunteers.

Oral Contraceptives

A placebo-controlled study in 29 healthy female subjects showed that moxifloxacin 400 mg daily for 7 days did not interfere with the hormonal suppression of oral contraception with 0.15 mg levonorgestrel/0.03 mg ethinylestradiol (as measured by serum progesterone, FSH, estradiol, and LH), or with the pharmacokinetics of the administered contraceptive agents.

Probenecid

Probenecid (500 mg twice daily for two days) did not alter the renal clearance and total amount of moxifloxacin (400 mg single dose) excreted renally in a study of 12 healthy volunteers.

Ranitidine

No significant effect of ranitidine (150 mg twice daily for three days as pretreatment) on the pharmacokinetics of moxifloxacin (400 mg single dose) was detected in a study involving 10 healthy volunteers.

Theophylline

No significant effect of moxifloxacin (200 mg every twelve hours for 3 days) on the pharmacokinetics of theophylline (400 mg every twelve hours for 3 days) was detected in a study involving 12 healthy volunteers. In addition, theophylline was not shown to affect the pharmacokinetics of moxifloxacin. The effect of co-administration of 400 mg once daily of moxifloxacin with theophylline has not been studied.

Warfarin

No significant effect of moxifloxacin (400 mg once daily for eight days) on the pharmacokinetics of R- and S-warfarin (25 mg single dose of warfarin sodium on the fifth day) was detected in a study involving 24 healthy volunteers. No significant change in prothrombin time was observed. However, fluoroquinolones, including Moxifloxacin Hydrochloride, have been reported to enhance the anticoagulant effects of warfarin or its derivatives in the patient population [see Adverse Reactions (6.2) and Drug Interactions (7.2)].

12.4 Microbiology

Mechanism of Action

The bactericidal action of moxifloxacin results from inhibition of the topoisomerase II (DNA gyrase) and topoisomerase IV required for bacterial DNA replication, transcription, repair, and recombination.

Resistance

The mechanism of action for fluoroquinolones, including moxifloxacin, is different from that of macrolides, beta-lactams, aminoglycosides, or tetracyclines; therefore, microorganisms resistant to these classes of drugs may be susceptible to moxifloxacin. Resistance to fluoroquinolones occurs primarily by a mutation in topoisomerase II (DNA gyrase) or topoisomerase IV genes, decreased outer membrane permeability or drug efflux. In vitro resistance to moxifloxacin develops slowly via multiple-step mutations. Resistance to moxifloxacin occurs in vitro at a general frequency of between 1.8 x 10–9to < 1 x 10–11 for Gram-positive bacteria.

Cross Resistance

Gram-positive bacteria

Enterococcus faecalis

Staphylococcus aureus

Streptococcus anginosus

Streptococcus constellatus

Streptococcus pneumoniae (including multi-drug resistant isolates [MDRSP] **)

Streptococcus pyogenes

**MDRSP, Multi-drug resistant Streptococcus pneumoniae includes isolates previously known as PRSP (Penicillin-resistant S. pneumoniae), and are isolates resistant to two or more of the following antibiotics: penicillin (MIC) ≥2 mcg/mL), 2nd generation cephalosporins (for example, cefuroxime), macrolides, tetracyclines, and trimethoprim/sulfamethoxazole.

Gram-negative bacteria

Enterobacter cloacae

Escherichia coli

Haemophilus influenzae

Haemophilus parainfluenzae

Klebsiella pneumoniae

Moraxella catarrhalis

Proteus mirabilis

Yersinia pestis

Anaerobic bacteria

Bacteroides fragilis

Bacteroides thetaiotaomicron

Clostridium perfringens

Peptostreptococcus species

Other microorganisms

Chlamydophila pneumoniae

Mycoplasma pneumoniae

The following in vitro data are available, but their clinical significance is unknown. At least 90 percent of the following bacteria exhibit an in vitro minimum inhibitory concentration (MIC) less than or equal to the susceptible breakpoint for moxifloxacin. However, the efficacy of Moxifloxacin Hydrochloride in treating clinical infections due to these bacteria has not been established in adequate and well controlled clinical trials.

Gram-positive bacteria

Staphylococcus epidermidis

Streptococcus agalactiae

Streptococcus viridans group

Gram-negative bacteria

Citrobacter freundii

Klebsiella oxytoca

Legionella pneumophila

Anaerobic bacteria

Fusobacterium species

Prevotella species

Susceptibility Tests Methods

When available, the clinical microbiology laboratory should provide the results of in vitro susceptibility test results for antimicrobial drug products used in resident hospitals to the physician as periodic reports that describe the susceptibility profile of nosocomial and community acquired pathogens. These reports should aid the physician in selecting an antibacterial drug product for treatment.

Dilution Techniques

Quantitative methods are used to determine antimicrobial minimum inhibitory concentrations (MICs). These MICs provide estimates of the susceptibility of bacteria to antimicrobial compounds. The MICs should be determined using a standardized procedure. Standardized procedures are based on a dilution method (broth and/or agar). 1,2,4 The MIC values should be interpreted according to the criteria in Table 10.

Diffusion Techniques

Quantitative methods that require measurement of zone diameters can also provide reproducible estimates of the susceptibility of bacteria to antimicrobial compounds. The zone size provides an estimate of the susceptibility of bacteria to antimicrobial compounds. The zone size prove should be determined using a standardized test method.2,3 This procedure uses paper disks impregnated with 5 mcg moxifloxacin to test the susceptibility of bacteria to moxifloxacin. The disc diffusion interpretive criteria are provided in Table 10.

Anaerobic Techniques

For anaerobic bacteria, the susceptibility to moxifloxacin can be determined by a standardized test method.2,5 The MIC values obtained should be interpreted according to the criteria provided in Table 10.

Table 10: Susceptibility Test Interpretive Criteria for Moxifloxacin

MIC (mcg/mL)

Zone Diameter (mm)

Species

S

I

R

S

I

R

Enterobacteriaceae

≤2

4

≥8

≥19

16–18

≤15

Enterococcus faecalis

≤1

2

≥4

≥18

15–17

≤14

Staphylococcus aureus

≤0.5

1

≥2

≥24

21–23

≤20

Haemophilus influenzae

≤1

a

a

≥18

a

a

Haemophilus parainfluenzae

≤1

a

a

≥18

a

a

Streptococcus pneumoniae

≤1

2

≥4

≥18

15–17

≤14

Streptococcus species

≤1

2

≥4

≥18

15–17

≤14

Anaerobic bacteria

≤2

4

≥8

-

-

-

Yersinia pestis

≤0.25

a

a

-

-

-

S=susceptible, I=Intermediate, and R=resistant.
a) The current absence of data on moxifloxacin-resistant isolates precludes defining any results other than “Susceptible”. Isolates yielding test results (MIC or zone diameter) other than susceptible, should be submitted to a reference laboratory for additional testing.

A report of “Susceptible” indicates that the antimicrobial is likely to inhibit growth of the pathogen if the antimicrobial compound reaches the concentrations at the infection site necessary to inhibit growth of the pathogen. A report of “Intermediate” indicates that the result should be considered equivocal, and, if the microorganism is not fully susceptible to alternative, clinically feasible drugs, the test should be repeated. This category implies possible clinical applicability in body sites where the drug is physiologically concentrated or in situations where a high dosage of the drug product can be used. This category also provides a buffer zone that prevents small uncontrolled technical factors from causing major discrepancies in interpretation. A report of “Resistant” indicates that the antimicrobial is not likely to inhibit growth of the pathogen if the antimicrobial compound reaches the concentrations usually achievable at the infection site; other therapy should be selected.

Quality Control

Standardized susceptibility test procedures require the use of laboratory controls to monitor and ensure the accuracy and precision of supplies and reagents used in the assay and the techniques of the individuals performing the test.1,2,3,4,5 Standard moxifloxacin powder should provide the following range of MIC values noted in Table 11. For the diffusion technique using the 5 mcg moxifloxacin disk, the criteria in Table 11 should be achieved.

Table 11: Acceptable Quality Control Ranges for Moxifloxacin

Strains

MIC range
(mcg/mL)

Zone Diameter (mm)

Enterococcus faecalis ATCC 29212

0.06–0.5

-

Escherichia coli ATCC 25922

0.008–0.06

28–35

Haemophilus influenzae ATCC 49247

0.008–0.03

31–39

Staphylococcus aureus ATCC 29213

0.015–0.12

-

Staphylococcus aureus ATCC 25923

-

28–35

Streptococcus pneumoniae ATCC 49619

0.06–0.25

25–31

Bacteroides fragilis ATCC 25285

0.125–0.5

-

Bacteroides thetaiotaomicron ATCC 29741

1–4

-

Eubacterium lentum ATCC 43055

0.125–0.5

-

13 NONCLINICAL TOXICOLOGY

13.1 Carcinogenesis, Mutagenesis, Impairment of Fertility

Long term studies in animals to determine the carcinogenic potential of moxifloxacin have not been performed.

Moxifloxacin was not mutagenic in 4 bacterial strains (TA 98, TA 100, TA 1535, TA 1537) used in the Ames Salmonella reversion assay. As with other fluoroquinolones, the positive response observed with moxifloxacin in strain TA 102 using the same assay may be due to the inhibition of DNA gyrase. Moxifloxacin was not mutagenic in the CHO/HGPRT mammalian cell gene mutation assay. An equivocal result was obtained in the same assay when v79 cells were used. Moxifloxacin was clastogenic in the v79 chromosome aberration assay, but it did not induce unscheduled DNA synthesis in cultured rat hepatocytes. There was no evidence of genotoxicity in vivo in a micronucleus test or a dominant lethal test in mice.

Moxifloxacin had no effect on fertility in male and female rats at oral doses as high as 500 mg/kg/day, approximately 12 times the maximum recommended human dose based on body surface area) or at intravenous doses as high as 45 mg/kg/day, approximately equal to the maximum recommended human dose based on body surface area). At 500 mg/kg orally there were slight effects on sperm morphology (head-tail separation) in male rats and on the estrous cycle in female rats.

13.2 Animal Toxicology and/or Pharmacology

Fluoroquinolones have been shown to cause arthropathy in immature animals. In studies in juvenile dogs oral doses of moxifloxacin 30 mg/kg/day or more (approximately 1.5 times the maximum recommended human dose based upon systemic exposure) for 28 days resulted in arthropathy. There was no evidence of arthropathy in mature monkeys and rats at oral doses up to 135 and 500 mg/kg/day, respectively.

Moxifloxacin at an oral dose of 300 mg/kg did not show an increase in acute toxicity or potential for CNS toxicity (for example, seizures) in mice when used in combination with NSAIDs such as diclofenac, ibuprofen, or fenbufen. Some fluoroquinolones have been reported to have proconvulsant activity that is exacerbated with concomitant use of NSAIDs.

A QT-prolonging effect of moxifloxacin was found in dog studies, at plasma concentrations about five times the human therapeutic level. The combined infusion of sotalol, a Class III antiarrhythmic agent, with moxifloxacin induced a higher degree of QTc prolongation in dogs than that induced by the same dose (30 mg/kg) of moxifloxacin alone. Electrophysiological in vitro studies suggested an inhibition of the rapid activating component of the delayed rectifier potassium current (IKr) as an underlying mechanism.

No signs of local intolerability were observed in dogs when moxifloxacin was administered intravenously. After intra-arterial injection, inflammatory changes involving the peri-arterial soft tissue were observed suggesting that intra-arterial administration of Moxifloxacin Hydrochloride should be avoided.

14 CLINICAL STUDIES

14.1 Acute Bacterial Sinusitis

In a controlled double-blind study conducted in the US, Moxifloxacin Hydrochloride Tablets (400 mg once daily for ten days) were compared with cefuroxime axetil (250 mg twice daily for ten days) for the treatment of acute bacterial sinusitis. The trial included 457 patients valid for the efficacy analysis. Clinical success (cure plus improvement) at the 7 to 21 day post-therapy test of cure visit was 90% for Moxifloxacin Hydrochloride and 89% for cefuroxime.

An additional non-comparative study was conducted to gather bacteriological data and to evaluate microbiological eradication in adult patients treated with Moxifloxacin Hydrochloride 400 mg once daily for seven days. All patients (n = 336) underwent antral puncture in this study. Clinical success rates and eradication/presumed eradication rates at the 21 to 37 day follow-up visit were 97% (29 out of 30) for Streptococcus pneumoniae, 83% (15 out of 18) for Moraxella catarrhalis, and 80% (24 out of 30) for Haemophilus influenzae.

14.2 Acute Bacterial Exacerbation of Chronic Bronchitis

Moxifloxacin Hydrochloride Tablets (400 mg once daily for five days) were evaluated for the treatment of acute bacterial exacerbation of chronic bronchitis in a randomized, double-blind, controlled clinical trial conducted in the US. This study compared Moxifloxacin Hydrochloride with clarithromycin (500 mg twice daily for 10 days) and enrolled 629 patients. Clinical success was assessed at 7-17 days post-therapy. The clinical success for Moxifloxacin Hydrochloride was 89% (222/250) compared to 89% (224/251) for clarithromycin.

Table 12: Clinical Success Rates at Follow-Up Visit for Clinically Evaluable Patients by Pathogen

(Acute Bacterial Exacerbation of Chronic Bronchitis)

PATHOGEN

Moxifloxacin Hydrochloride

Clarithromycin

Streptococcus pneumoniae

16/16 (100%)

20/23 (87%)

Haemophilus influenzae

33/37 (89%)

36/41 (88%)

Haemophilus parainfluenzae

16/16 (100%)

14/14 (100%)

Moraxella catarrhalis

29/34 (85%)

24/24 (100%)

Staphylococcus aureus

15/16 (94%)

6/8 (75%)

Klebsiella pneumoniae

18/20 (90%)

10/11 (91%)

The microbiological eradication rates (eradication plus presumed eradication) in Moxifloxacin Hydrochloride treated patients were Streptococcus pneumoniae 100%, Haemophilus influenzae 89%, Haemophilus parainfluenzae 100%, Moraxella catarrhalis 85%, Staphylococcus aureus 94%, and Klebsiella pneumoniae 85%.

14.3 Community Acquired Pneumonia

A randomized, double-blind, controlled clinical trial was conducted in the US to compare the efficacy of Moxifloxacin Hydrochloride Tablets (400 mg once daily) to that of high-dose clarithromycin (500 mg twice daily) in the treatment of patients with clinically and radiologically documented community acquired pneumonia. This study enrolled 474 patients (382 of whom were valid for the efficacy analysis conducted at the 14–35 day follow-up visit). Clinical success for clinically evaluable patients was 95% (184/194) for Moxifloxacin Hydrochloride and 95% (178/188) for high dose clarithromycin.

A randomized, double-blind, controlled trial was conducted in the US and Canada to compare the efficacy of sequential intravenous/oral Moxifloxacin Hydrochloride 400 mg once a day for 7–14 days to an intravenous/oral fluoroquinolone control (trovafloxacin or levofloxacin) in the treatment of patients with clinically and radiologically documented community acquired pneumonia. This study enrolled 516 patients, 362 of whom were valid for the efficacy analysis conducted at the 7-30 day post-therapy visit. The clinical success rate was 86% (157/182) for Moxifloxacin Hydrochloride therapy and 89% (161/180) for the fluoroquinolone comparators.

An open-label ex-US study that enrolled 628 patients compared Moxifloxacin Hydrochloride to sequential intravenous/oral amoxicillin/clavulanate (1.2 gram intravenously every 8 hours/625 mg orally every 8 hours) with or without high-dose intravenous/oral clarithromycin (500 mg twice a day). The intravenous formulations of the comparators are not FDA approved. The clinical success rate at Day 5–7 for Moxifloxacin Hydrochloride therapy was 93% (241/258) and demonstrated superiority to amoxicillin/clavulanate ± clarithromycin (85%, 239/280) [95% C.I. of difference in success rates between moxifloxacin and comparator (2.9%, 13.2%)]. The clinical success rate at the 21–28 days post-therapy visit for Moxifloxacin Hydrochloride was 84% (216/258), which also demonstrated superiority to the comparators (74%, 208/280) [95% C.I. of difference in success rates between moxifloxacin and comparator (2.6%, 16.3%)].

The clinical success rates by pathogen across four CAP studies are presented in Table 13.

Table 13: Clinical Success Rates By Pathogen (Pooled CAP Studies)

PATHOGEN

Moxifloxacin Hydrochloride

Streptococcus pneumoniae

80/85

(94%)

Staphylococcus aureus

17/20

(85%)

Klebsiella pneumoniae

11/12

(92%)

Haemophilus influenzae

56/61

(92%)

Chlamydophila pneumoniae

119/128

(93%)

Mycoplasma pneumoniae

73/76

(96%)

Moraxella catarrhalis

11/12

(92%)

Community Acquired Pneumonia caused by Multi-Drug Resistant Streptococcus pneumoniae (MDRSP)*

Moxifloxacin Hydrochloride was effective in the treatment of community acquired pneumonia (CAP) caused by multi-drug resistant Streptococcus pneumoniae MDRSP* isolates. Of 37 microbiologically evaluable patients with MDRSP isolates, 35 patients (95%) achieved clinical and bacteriological success post-therapy. The clinical and bacteriological success rates based on the number of patients treated are shown in Table 14.

* MDRSP, Multi-drug resistant Streptococcus pneumoniae includes isolates previously known as PRSP (Penicillin-resistant S. pneumoniae), and are isolates resistant to two or more of the following antibiotics: penicillin (MIC ≥ 2 mcg/mL), 2nd generation cephalosporins (for example, cefuroxime), macrolides, tetracyclines, and trimethoprim/sulfamethoxazole.

Table 14: Clinical and Bacteriological Success Rates for Moxifloxacin Hydrochloride-Treated MDRSP CAP Patients (Population: Valid for Efficacy)

Screening Susceptibility

Clinical Success

Bacteriological Success

n/Na

%

n/Nb

%

Penicillin-resistant

21/21

100%c

21/21

100%c

2nd generation cephalosporin-resistant

25/26

96%c

25/26

96%c

Macrolide-resistantd

22/23

96%

22/23

96%

Trimethoprim/sulfamethoxazole-resistant

28/30

93%

28/30

93%

Tetracycline-resistant

17/18

94%

17/18

94%

a)
n = number of patients successfully treated; N = number of patients with MDRSP (from a total of 37 patients)
b)
n = number of patients successfully treated (presumed eradication or eradication); N = number of patients with MDRSP (from a total of 37 patients)
c)
One patient had a respiratory isolate that was resistant to penicillin and cefuroxime but a blood isolate that was intermediate to penicillin and cefuroxime. The patient is included in the database based on the respiratory isolate.
d)
Azithromycin, clarithromycin, and erythromycin were the macrolide antimicrobials tested.

Not all isolates were resistant to all antimicrobial classes tested. Success and eradication rates are summarized in Table 15.

Table 15: Clinical Success Rates and Microbiological Eradication Rates for Resistant Streptococcus pneumoniae (Community Acquired Pneumonia)

S. pneumoniae with
MDRSP

Clinical Success

Bacteriological
Eradication Rate

Resistant to 2 antimicrobials

12/13 (92.3 %)

12/13 (92.3 %)

Resistant to 3 antimicrobials

10/11 (90.9 %)a

10/11 (90.9 %)a

Resistant to 4 antimicrobials

6/6 (100%)

6/6 (100%)

Resistant to 5 antimicrobials

7/7 (100%)a

7/7 (100%)a

Bacteremia with MDRSP

9/9 (100%)

9/9 (100%)

a)
One patient had a respiratory isolate resistant to 5 antimicrobials and a blood isolate resistant to 3 antimicrobials. The patient was included in the category resistant to 5 antimicrobials.

14.4 Uncomplicated Skin and Skin Structure Infections

A randomized, double-blind, controlled clinical trial conducted in the US compared the efficacy of Moxifloxacin Hydrochloride 400 mg once daily for seven days with cephalexin HCl 500 mg three times daily for seven days. The percentage of patients treated for uncomplicated abscesses was 30%, furuncles 8%, cellulitis 16%, impetigo 20%, and other skin infections 26%. Adjunctive procedures (incision and drainage or debridement) were performed on 17% of the Moxifloxacin Hydrochloride treated patients and 14% of the comparator treated patients. Clinical success rates in evaluable patients were 89% (108/122) for Moxifloxacin Hydrochloride and 91% (110/121) for cephalexin HCl.

14.5 Complicated Skin and Skin Structure Infections

Two randomized, active controlled trials of cSSSI were performed. A double-blind trial was conducted primarily in North America to compare the efficacy of sequential intravenous/oral Moxifloxacin Hydrochloride 400 mg once a day for 7-14 days to an intravenous/oral beta-lactam/beta-lactamase inhibitor control in the treatment of patients with cSSSI. This study enrolled 617 patients, 335 of which were valid for the efficacy analysis. A second open-label International study compared Moxifloxacin Hydrochloride 400 mg once a day for 7-21 days to sequential intravenous/oral beta-lactam/beta-lactamase inhibitor control in the treatment of patients with cSSSI. This study enrolled 804 patients, 632 of which were valid for the efficacy analysis. Surgical incision and drainage or debridement was performed on 55% of the Moxifloxacin Hydrochloride treated and 53% of the comparator treated patients in these studies and formed an integral part of therapy for this indication. Success rates varied with the type of diagnosis ranging from 61% in patients with infected ulcers to 90% in patients with complicated erysipelas. These rates were similar to those seen with comparator drugs. The overall success rates in the evaluable patients and the clinical success by pathogen are shown in Tables 16 and 17.

Table 16: Overall Clinical Success Rates in Patients with Complicated Skin and Skin Structure Infections

Study

Moxifloxacin Hydrochloride
n/N (%)

Comparator
n/N (%)

95% Confidence
Interval a

North America

125/162 (77.2%)

141/173 (81.5%)

(-14.4%, 2%)

International

254/315 (80.6%)

268/317 (84.5%)

(-9.4%, 2.2%)

a)
of difference in success rates between Moxifloxacin and comparator (Moxifloxacin – comparator)

Table 17: Clinical Success Rates by Pathogen in Patients with Complicated Skin and Skin Structure Infections

Pathogen

Moxifloxacin Hydrochloride
n/ N (%)

Comparator
n/N (%)

Staphylococcus aureus (methicillin-susceptible isolates)a

106/129 (82.2%)

120/137 (87.6%)

Escherichia coli

31/38 (81.6 %)

28/33 (84.8 %)

Klebsiella pneumoniae

11/12 (91.7 %)

7/10 (70%)

Enterobacter cloacae

9/11 (81.8%)

4/7 (57.1%)

a)
methicillin susceptibility was only determined in the North American Study

14.6 Complicated Intra-Abdominal Infections

Two randomized, active controlled trials of cIAI were performed. A double-blind trial was conducted primarily in North America to compare the efficacy of sequential intravenous/oral Moxifloxacin Hydrochloride 400 mg once a day for 5–14 days to intravenous/piperacillin/tazobactam followed by oral amoxicillin/clavulanic acid in the treatment of patients with cIAI, including peritonitis, abscesses, appendicitis with perforation, and bowel perforation. This study enrolled 681 patients, 379 of which were considered clinically evaluable. A second open-label international study compared Moxifloxacin Hydrochloride 400 mg once a day for 5–14 days to intravenous ceftriaxone plus intravenous metronidazole followed by oral amoxicillin/clavulanic acid in the treatment of patients with cIAI. This study enrolled 595 patients, 511 of which were considered clinically evaluable. The clinically evaluable population consisted of subjects with a surgically confirmed complicated infection, at least 5 days of treatment and a 25–50 day follow-up assessment for patients at the Test of Cure visit. The overall clinical success rates in the clinically evaluable patients are shown in Table 18.

Table 18: Clinical Success Rates in Patients with Complicated Intra-Abdominal Infections

Study

Moxifloxacin Hydrochloride
n/ N (%)

Comparator
n/N (%)

95% Confidence
Intervala

North America (overall)

146/183 (79.8%)

153/196 (78.1%)

(-7.4%, 9.3%)

Abscess

40/57 (70.2%)

49/63 (77.8%)b

NAc

Non-abscess

106/126 (84.1%)

104/133 (78.2%)

NA

International (overall)

199/246 (80.9%)

218/265 (82.3%)

(-8.9%, 4.2%)

Abscess

73/93 (78.5%)

86/99 (86.9%)

NA

Non-abscess

126/153 (82.4%)

132/166 (79.5%)

NA

a)
of difference in success rates between Moxifloxacin Hydrochloride and comparator (Moxifloxacin Hydrochloride – comparator)
b)
Excludes 2 patients who required additional surgery within the first 48 hours.
c)
NA - not applicable

14.7 Plague

Efficacy studies of Moxifloxacin Hydrochloride could not be conducted in humans with pneumonic plague for ethical and feasibility reasons. Therefore, approval of this indication was based on an efficacy study conducted in animals and supportive pharmacokinetic data in adult humans and animals.

A randomized, blinded, placebo-controlled study was conducted in an African Green Monkey (AGM) animal model of pneumonic plague. Twenty AGM (10 males and 10 females) were exposed to an inhaled mean (± SD) dose of 100 ± 50 LD50 (range 92 to 127 LD50) of Yersinia pestis (CO92 strain) aerosol. The minimal inhibitory concentration (MIC) of moxifloxacin for the Y. pestis strain used in this study was 0.06 mcg/mL. Development of sustained fever for at least 4 hours duration was used as the trigger for the initiation of 10 days of treatment with either a humanized regimen of moxifloxacin or placebo. All study animals were febrile and bacteremic with Y. pestis prior to the initiation of study treatment. Ten of 10 (100%) of the animals receiving the placebo succumbed to disease between 83 to 139 h (mean 115 ± 19 hours) post treatment. Ten of 10 (100%) moxifloxacin-treated animals survived for the 30-day period after completion of the study treatment. Compared to the placebo group, mortality in the moxifloxacin group was significantly lower (difference in survival: 100% with a two-sided 95% exact confidence interval [66.3%, 100%], p-value<0.0001).

The mean plasma concentrations of moxifloxacin associated with a statistically significant improvement in survival over placebo in an AGM model of pneumonic plague are reached or exceeded in human adults receiving the recommended oral and intravenous dosage regimens. The mean (± SD) peak plasma concentration (Cmax) and total plasma exposure defined as the area under the plasma concentration-time curve (AUC) in human adults receiving 400 mg intravenously were 3.9 ± 0.9 mcg/mL and 39.3 ± 8.6 mcg•h/mL, respectively [see Clinical Pharmacology (12.3)]. The mean (± SD) peak plasma concentration and AUC0-24 in AGM following one- day administration of a humanized dosing regimen simulating the human AUC0-24 at a 400 mg dose were 4.4 ± 1.5 mcg/mL and 22 ± 8.0 mcg·h/mL, respectively.

15 REFERENCES

1.
Clinical and Laboratory Standards Institute (CLSI), Methods for Dilution Antimicrobial Susceptibility Tests for Bacteria That Grow Aerobically Approved Standard – Tenth Edition. CLSI Document M7-A10 [2015], CLSI, 950 West Valley Rd., Suite 2500, Wayne, PA 19087, USA.
2.
Clinical and Laboratory Standards Institute (CLSI). Performance Standards for Antimicrobial Susceptibility Testing; Twenty-sixth Informational Supplement, CLSI document M100-S26 [2016], Clinical and Laboratory Standards Institute, 950 West Valley Road, Suite 2500, Wayne, Pennsylvania 19087, USA. .
3.
Clinical and Laboratory Standards Institute (CLSI). Performance Standards for Antimicrobial Disk Diffusion Susceptibility Tests; Approved Standard – Twelfth Edition. CLSI document M02-A12 [2015], Clinical and Laboratory Standards Institute, 950 West Valley Road, Suite 2500, Wayne, Pennsylvania 19087, USA.
4.
Clinical and Laboratory Standards Institute (CLSI). Methods for Antimicrobial Dilution and Disk Susceptibility Testing for Infrequently Isolated or Fastidious Bacteria: Approved Guidelines—Third Edition CLSI document M45-A3 [2016], Clinical and Laboratory Standards Institute, 950 West Valley Road, Suite 2500, Wayne, Pennsylvania 19087, USA.
5.
Clinical and Laboratory Standards Institute (CLSI). Methods for Antimicrobial Susceptibility Testing of Anaerobic Bacteria; Approved Standard - Eighth Edition. CLSI document M11-A8 [2012]. Clinical and Laboratory Standards Institute, 950 West Valley Road, Suite 2500, Wayne, Pennsylvania 19087, USA.

16 HOW SUPPLIED/STORAGE AND HANDLING

Moxifloxacin Hydrochloride (moxifloxacin hydrochloride) tablets are available as oblong, dull red film-coated tablets containing 400 mg moxifloxacin.

The tablet is coded with the word “BAYER” on one side and “M400” on the reverse side.

Bottles of 30: NDC 47781-268-30

Store at 25°C (77°F); excursions permitted to 15–30°C (59–86°F) [see USP Controlled Room Temperature]. Avoid high humidity.

17 PATIENT COUNSELING INFORMATION

Advise the patient to read the FDA-approved patient labeling (Medication Guide)

Serious Adverse Reactions

Advise patients to stop taking Moxifloxacin Hydrochloride if they experience an adverse reaction and to call their healthcare provider for advice on completing the full course of treatment with another antibacterial drug.

Inform patients of the following serious adverse reactions that have been associated with Moxifloxacin Hydrochloride or other fluoroquinolone use:

•
Disabling and potentially irreversible serious adverse reactions that may occur together: Inform patients that disabling and potentially irreversible serious adverse reactions, including tendinitis and tendon rupture, peripheral neuropathies, and central nervous system effects, have been associated with use of Moxifloxacin Hydrochloride and may occur together in the same patient. Inform patients to stop taking Moxifloxacin Hydrochloride immediately if they experience an adverse reaction and to call their healthcare provider.
•
Tendinitis and Tendon Rupture: Instruct patients to contact their healthcare provider if they experience pain, swelling, or inflammation of a tendon, or weakness or inability to use one of their joints; rest and refrain from exercise; and discontinue Moxifloxacin Hydrochloride treatment. Symptoms may be irreversible. The risk of severe tendon disorder with fluoroquinolones is higher in older patients usually over 60 years of age, in patients taking corticosteroid drugs, and in patients with kidney, heart or lung transplants.
•
Peripheral Neuropathies: Inform patients that peripheral neuropathies have been associated with Moxifloxacin Hydrochloride use, symptoms may occur soon after initiation of therapy and may be irreversible. If symptoms of peripheral neuropathy including pain, burning, tingling, numbness and/or weakness develop, immediately discontinue Moxifloxacin Hydrochloride and tell them to contact their physician.
•
Central nervous system effects (for example, convulsions, dizziness, lightheadedness, increased intracranial pressure) : Inform patients that convulsions have been reported in patients receiving fluoroquinolones, including Moxifloxacin Hydrochloride. Instruct patients to notify their physician before taking this drug if they have a history of convulsions. Inform patients that they should know how they react to Moxifloxacin Hydrochloride before they operate an automobile or machinery or engage in other activities requiring mental alertness and coordination. Instruct patients to notify their physician if persistent headache with or without blurred vision occurs.
•
Exacerbation of Myasthenia Gravis: Instruct patients to inform their physician of any history of myasthenia gravis. Instruct patients to notify their physician if they experience any symptoms of muscle weakness, including respiratory difficulties.
•
Hypersensitivity Reactions: Inform patients that Moxifloxacin Hydrochloride can cause hypersensitivity reactions, even following a single dose, and to discontinue the drug at the first sign of a skin rash, hives or other skin reactions, a rapid heartbeat, difficulty in swallowing or breathing, any swelling suggesting angioedema (for example, swelling of the lips, tongue, face, tightness of the throat, hoarseness), or other symptoms of an allergic reaction.
•
Hepatotoxicity: Inform patients that severe hepatotoxicity (including acute hepatitis and fatal events) has been reported in patients taking Moxifloxacin Hydrochloride. Instruct patients to inform their physician if they experience any signs or symptoms of liver injury including: loss of appetite, nausea, vomiting, fever, weakness, tiredness, right upper quadrant tenderness, itching, yellowing of the skin and eyes, light colored bowel movements or dark colored urine.
•
Diarrhea: Diarrhea is a common problem caused by antibiotics which usually ends when the antibiotic is discontinued. Sometimes after starting treatment with antibiotics, patients can develop watery and bloody stools (with or without stomach cramps and fever) even as late as two or more months after having taken the last dose of the antibiotic. If this occurs, instruct patients to contact their physician as soon as possible.
•
Prolongation of the QT Interval: Instruct patients to inform their physician of any personal or family history of QT prolongation or proarrhythmic conditions such as hypokalemia, bradycardia, or recent myocardial ischemia; if they are taking any Class IA (quinidine, procainamide), or Class III (amiodarone, sotalol) antiarrhythmic agents. Instruct patients to notify their physician if they have any symptoms of prolongation of the QT interval, including prolonged heart palpitations or a loss of consciousness.
•
Photosensitivity/Phototoxicity: Inform patients that photosensitivity/phototoxicity has been reported in patients receiving fluoroquinolones. Inform patients to minimize or avoid exposure to natural or artificial sunlight (tanning beds or UVA/B treatment) while taking quinolones. If patients need to be outdoors while using quinolones, instruct them to wear loose-fitting clothes that protect skin from sun exposure and discuss other sun protection measures with their physician. If a sunburn-like reaction or skin eruption occurs, instruct patients to contact their physician.
•
Blood Glucose Disturbances: Inform the patients that if they are diabetic and are being treated with insulin or an oral hypoglycemic agent and a hypoglycemic reaction occurs, they should discontinue Moxifloxacin Hydrochloride and consult a physician.

Antibacterial Resistance

Inform patients that antibacterial drugs including Moxifloxacin Hydrochloride should only be used to treat bacterial infections. They do not treat viral infections (for example, the common cold). When Moxifloxacin Hydrochloride is prescribed to treat a bacterial infection, patients should be told that although it is common to feel better early in the course of therapy, the medication should be taken exactly as directed. Skipping doses or not completing the full course of therapy may (1) decrease the effectiveness of the immediate treatment and (2) increase the likelihood that bacteria will develop resistance and will not be treatable by Moxifloxacin Hydrochloride or other antibacterial drugs in the future.

Administration With Food, Fluids, and Drug Products Containing Multivalent Cations

Inform patients that Moxifloxacin Hydrochloride tablets may be taken with or without food. Advise patients drink fluids liberally.

Inform patients that Moxifloxacin Hydrochloride tablets should be taken at least 4 hours before or 8 hours after multivitamins (containing iron or zinc), antacids (containing magnesium or aluminum), sucralfate, or didanosine buffered tablets for oral suspension or the pediatric powder for oral solution.

Plague Studies

Inform patients given Moxifloxacin Hydrochloride for plague that efficacy studies could not be conducted in humans for feasibility reasons. Therefore, approval for plague was based on efficacy studies conducted in animals.

MEDICATION GUIDE

FDA-Approved Medication Guide

MEDICATION GUIDE

Moxifloxacin Hydrochloride
Tablets

Read the Medication Guide that comes with Moxifloxacin Hydrochloride® before you start taking it and each time you get a refill. There may be new information. This Medication Guide does not take the place of talking to your healthcare provider about your medical condition or your treatment.

What is the most important information I should know about Moxifloxacin Hydrochloride?

Moxifloxacin Hydrochloride belongs to a class of antibiotics called fluoroquinolones. Moxifloxacin Hydrochloride can cause serious side effects that can happen at the same time and could result in death. If you get any of the following serious side effects, you should stop taking Moxifloxacin Hydrochloride and get medical help right away. Talk with your healthcare provider about whether you should continue to take Moxifloxacin Hydrochloride.

1. Tendon rupture or swelling of the tendon (tendinitis).

•
Tendon problems can happen in people of all ages who take Moxifloxacin Hydrochloride. Tendons are tough cords of tissue that connect muscles to bones. Symptoms of tendon problems may include:
•
Pain, swelling, tears and inflammation of tendons including the back of the ankle (Achilles), shoulder, hand, or other tendon sites.
•
The risk of getting tendon problems while you take Moxifloxacin Hydrochloride is higher if you:
o
Are over 60 years of age
o
Are taking steroids (corticosteroids)
o
Have had a kidney, heart or lung transplant
•
Tendon problems can happen in people who do not have the above risk factors when they take Moxifloxacin Hydrochloride.
•
Other reasons that can increase your risk of tendon problems can include:
o
Physical activity or exercise
o
Kidney failure
o
Tendon problems in the past, such as in people with rheumatoid arthritis (RA).
•
Stop taking Moxifloxacin Hydrochloride immediately and call your healthcare provider right away at the first sign of tendon pain, swelling or inflammation. Stop taking Moxifloxacin Hydrochloride until tendinitis or tendon rupture has been ruled out by your healthcare provider. Avoid exercise and using the affected area. The most common area of pain and swelling is in the Achilles tendon at the back of your ankle. This can also happen with other tendons.
•
Talk to your healthcare provider about the risk of tendon rupture with continued use of Moxifloxacin Hydrochloride. You may need a different antibiotic that is not a fluoroquinolone to treat your infection.
•
Tendon rupture can happen while you are taking or after you have finished taking Moxifloxacin Hydrochloride. Tendon ruptures can happen within hours or days after taking Moxifloxacin Hydrochloride and have happened up to several months after patients have finished taking their fluoroquinolone.
•
Stop taking Moxifloxacin Hydrochloride immediately and get medical help right away if you get any of the following signs or symptoms of a tendon rupture:
o
Hear or feel a snap or pop in a tendon area
o
Bruising right after an injury in a tendon area
o
Unable to move the affected area or bear weight.
2. Changes in sensation and possible nerve damage (Peripheral Neuropathy). Damage to the nerves in arms, hands, legs, or feet can happen in people who take fluoroquinolones, including Moxifloxacin Hydrochloride. Stop taking Moxifloxacin Hydrochloride immediately and talk to your healthcare provider right away if you get any of the following symptoms of peripheral neuropathy in your arms, hands, legs, or feet:
•
pain
•
burning
•
tingling
•
numbness
•
weakness
Moxifloxacin Hydrochloride may need to be stopped to prevent permanent nerve damage.
3.
Central Nervous System (CNS) effects. Seizures have been reported in people who take fluoroquinolone antibacterial medicines, including Moxifloxacin Hydrochloride. Tell your healthcare provider if you have a history of seizures before you start taking Moxifloxacin Hydrochloride. CNS side effects may happen as soon as after taking the first dose of Moxifloxacin Hydrochloride. Stop taking Moxifloxacin Hydrochloride immediately and talk to your healthcare provider right away if you get any of these side effects, or other changes in mood or behavior:
•
seizures
•
hear voices, see things, or sense things that are not there (hallucinations)
•
feel restless
•
tremors
•
feel anxious or nervous
•
confusion
•
depression
•
trouble sleeping
•
nightmares
•
feel lightheaded or dizzy
•
feel more suspicious (paranoia)
•
suicidal thoughts or acts
•
headaches that will not go away, with or without blurred vision
4. Worsening of myasthenia gravis (a disease which causes muscle weakness). Fluoroquinolones like Moxifloxacin Hydrochloride may cause worsening of myasthenia gravis symptoms, including muscle weakness and breathing problems. Tell your healthcare provider if you have a history of myasthenia gravis before you start taking Moxifloxacin Hydrochloride. Call your healthcare provider right away if you have any worsening muscle weakness or breathing problems.
•
See the section “ What are the possible side effects of Moxifloxacin Hydrochloride?” for more information about side effects.

What is Moxifloxacin Hydrochloride?

Moxifloxacin Hydrochloride is a fluoroquinolone antibiotic medicine used to treat certain types of infections caused by certain germs called bacteria in adults 18 years or older. These bacterial infections include:

•
Community Acquired Pneumonia
•
Uncomplicated Skin and Skin Structure Infections
•
Complicated Skin and Skin Structure Infections
•
Complicated Intra-Abdominal Infections
•
Plague
•
Acute Bacterial Sinusitis
•
Acute Bacterial Exacerbation of Chronic Bronchitis

Moxifloxacin Hydrochloride should not be used in patients with acute bacterial sinusitis or acute bacterial exacerbation of chronic bronchitis if there are other treatment options available.

Studies of Moxifloxacin Hydrochloride for use in the treatment of plague were done in animals only, because plague could not be studied in people.

It is not known if Moxifloxacin Hydrochloride is safe and works in people under 18 years of age. Children have a higher chance of getting bone, joint, and tendon (musculoskeletal) problems while taking fluoroquinolone antibiotic medicines.

Sometimes infections are caused by viruses rather than by bacteria. Examples include viral infections in the sinuses and lungs, such as the common cold or flu. Antibiotics, including Moxifloxacin Hydrochloride, do not kill viruses.

Call your healthcare provider if you think your condition is not getting better while you are taking Moxifloxacin Hydrochloride.

Who should not take Moxifloxacin Hydrochloride?

Do not take Moxifloxacin Hydrochloride if you have ever had a severe allergic reaction to an antibiotic known as a fluoroquinolone, or if you are allergic to any of the ingredients in Moxifloxacin Hydrochloride. Ask your healthcare provider if you are not sure. See the list of ingredients in Moxifloxacin Hydrochloride at the end of this Medication Guide.

What should I tell my healthcare provider before taking Moxifloxacin Hydrochloride?

See “What is the most important information I should know about Moxifloxacin Hydrochloride?”

Tell your healthcare provider about all your medical conditions, including if you:

•
Have tendon problems; Moxifloxacin Hydrochloride should not be used in patients who have a history of tendon problems
•
Have a disease that causes muscle weakness (myasthenia gravis); Moxifloxacin Hydrochloride should not be used in patients who have a history of myasthenia gravis
•
Have central nervous system problems (such as epilepsy)
•
Have nerve problems; Moxifloxacin Hydrochloride should not be used in patients who have a history of a nerve problem called peripheral neuropathy
•
Have or anyone in your family has an irregular heartbeat, especially a condition called “QT prolongation”
•
Have low blood potassium (hypokalemia)
•
Have a slow heartbeat (bradycardia)
•
Have a history of seizures
•
Have kidney problems
•
Have rheumatoid arthritis (RA) or other history of joint problems
•
Are pregnant or planning to become pregnant. It is not known if Moxifloxacin Hydrochloride will harm your unborn child
•
Are breast-feeding or planning to breast-feed. It is not known if Moxifloxacin Hydrochloride passes into breast milk. You and your healthcare provider should decide whether you will take Moxifloxacin Hydrochloride or breast-feed.
•
Have diabetes or problems with low blood sugar (hypoglycemia).

Tell your healthcare provider about all the medicines you take, including prescription and non-prescription medicines, vitamins and herbal and dietary supplements. Moxifloxacin Hydrochloride and other medicines can affect each other causing side effects. Especially tell your healthcare provider if you take:

•
An NSAID (Non-Steroidal Anti-Inflammatory Drug). Many common medicines for pain relief are NSAIDs. Taking an NSAID while you take Moxifloxacin Hydrochloride or other fluoroquinolones may increase your risk of central nervous system effects and seizures. See “ What are the possible side effects of Moxifloxacin Hydrochloride?”
•
A blood thinner (warfarin, Coumadin, Jantoven).
•
A medicine to control your heart rate or rhythm (antiarrhythmic) See “ What are the possible side effects of Moxifloxacin Hydrochloride?”
•
An anti-psychotic medicine.
•
A tricyclic antidepressant.
•
An oral anti-diabetes medicine or insulin.
•
Erythromycin.
•
A water pill (diuretic).
•
A steroid medicine. Corticosteroids taken by mouth or by injection may increase the chance of tendon injury. See “ What is the most important information I should know about Moxifloxacin Hydrochloride?”
•
Certain medicines may keep Moxifloxacin Hydrochloride from working correctly. Take Moxifloxacin Hydrochloride either 4 hours before or 8 hours after taking these products:
o
An antacid, multivitamin, or other product that has magnesium, aluminum, iron, or zinc
o
Sucralfate (Carafate ®)
o
Didanosine oral suspension or solution

Ask your healthcare provider if you are not sure if any of your medicines are listed above.

Know the medicines you take. Keep a list of your medicines and show it to your healthcare provider and pharmacist when you get a new medicine.

How should I take Moxifloxacin Hydrochloride?

•
Take Moxifloxacin Hydrochloride once a day exactly as prescribed by your healthcare provider.
•
Take Moxifloxacin Hydrochloride at about the same time each day.
•
Moxifloxacin Hydrochloride Tablets should be swallowed.
•
Moxifloxacin Hydrochloride can be taken with or without food.
•
Drink plenty of fluids while taking Moxifloxacin Hydrochloride.
•
Moxifloxacin Hydrochloride Injection is given to you by intravenous infusion into your vein slowly, over 60 minutes, as prescribed by your healthcare provider.
•
Do not skip any doses, or stop taking Moxifloxacin Hydrochloride even if you begin to feel better, until you finish your prescribed treatment, unless:

o
You have tendon effects (see “ What is the most important information I should know about Moxifloxacin Hydrochloride?”).
o
You have nerve problems. See “What is the most important information I should know about Moxifloxacin Hydrochloride?”
o
You have central nervous system problems. See “What is the most important information I should know about Moxifloxacin Hydrochloride?”
o
You have a serious allergic reaction (see “What are the possible side effects of Moxifloxacin Hydrochloride?”), or your healthcare provider tells you to stop.

•
This will help make sure that all of the bacteria are killed and lower the chance that the bacteria will become resistant to Moxifloxacin Hydrochloride. If this happens, Moxifloxacin Hydrochloride and other antibiotic medicines may not work in the future.
•
If you miss a dose of Moxifloxacin Hydrochloride, take it as soon as you remember. Do not take more than 1 dose of Moxifloxacin Hydrochloride in one day.
•
If you take too much, call your healthcare provider or get medical help immediately.

What should I avoid while taking Moxifloxacin Hydrochloride?

•
Moxifloxacin Hydrochloride can make you feel dizzy and lightheaded. Do not drive, operate machinery, or do other activities that require mental alertness or coordination until you know how Moxifloxacin Hydrochloride affects you.
•
Avoid sunlamps, tanning beds, and try to limit your time in the sun. Moxifloxacin Hydrochloride can make your skin sensitive to the sun (photosensitivity) and the light from sunlamps and tanning beds. You could get severe sunburn, blisters or swelling of your skin. If you get any of these symptoms while taking Moxifloxacin Hydrochloride, call your healthcare provider right away. You should use a sunscreen and wear a hat and clothes that cover your skin if you have to be in sunlight.

What are the possible side effects of Moxifloxacin Hydrochloride?

Moxifloxacin Hydrochloride can cause side effects that may be serious or even cause death. See “What is the most important information I should know about Moxifloxacin Hydrochloride?”

Other serious side effects of Moxifloxacin Hydrochloride include:

Serious allergic reactions

•
Allergic reactions can happen in people taking fluoroquinolones, including Moxifloxacin Hydrochloride, even after only one dose. Stop taking Moxifloxacin Hydrochloride and get emergency medical help right away if you get any of the following symptoms of a severe allergic reaction:
•
Hives
•
Trouble breathing or swallowing
•
Swelling of the lips, tongue, face
•
Throat tightness, hoarseness
•
Rapid heartbeat
•
Faint
•
Yellowing of the skin or eyes. Stop taking Moxifloxacin Hydrochloride and tell your healthcare provider right away if you get yellowing of your skin or white part of your eyes, or if you have dark urine. These can be signs of a serious reaction to Moxifloxacin Hydrochloride (a liver problem).
•
Skin rash
Skin rash may happen in people taking Moxifloxacin Hydrochloride even after only one dose. Stop taking Moxifloxacin Hydrochloride at the first sign of a skin rash and call your healthcare provider. Skin rash may be a sign of a more serious reaction to Moxifloxacin Hydrochloride.
•
Serious heart rhythm changes (QT prolongation and torsade de pointes)
Tell your healthcare provider right away if you have a change in your heart beat (a fast or irregular heartbeat), or if you faint. Moxifloxacin Hydrochloride may cause a rare heart problem known as prolongation of the QT interval. This condition can cause an abnormal heartbeat and can be very dangerous. The chances of this event are higher in people:
o
Who are elderly
o
With a family history of prolonged QT interval
o
With low blood potassium (hypokalemia)
o
Who take certain medicines to control heart rhythm (antiarrhythmics)
•
Intestine infection (Pseudomembranous colitis)
Pseudomembranous colitis can happen with most antibiotics, including Moxifloxacin Hydrochloride. Call your healthcare provider right away if you get watery diarrhea, diarrhea that does not go away, or bloody stools. You may have stomach cramps and a fever. Pseudomembranous colitis can happen 2 or more months after you have finished your antibiotic.
•
Changes in blood sugar
People who take Moxifloxacin Hydrochloride and other fluoroquinolone medicines with oral anti-diabetes medicines or with insulin can get low blood sugar (hypoglycemia) and high blood sugar (hyperglycemia). Follow your healthcare provider's instructions for how often to check your blood sugar. If you have diabetes and you get low blood sugar while taking Moxifloxacin Hydrochloride, stop taking Moxifloxacin Hydrochloride and call your healthcare provider right away. Your antibiotic medicine may need to be changed.
•
Sensitivity to sunlight (photosensitivity)
See “ What should I avoid while taking Moxifloxacin Hydrochloride?” The most common side effects of Moxifloxacin Hydrochloride include nausea and diarrhea.

These are not all the possible side effects of Moxifloxacin Hydrochloride. Tell your healthcare provider about any side effect that bothers you or that does not go away. Call your doctor for medical advice about side effects. You may report side effects to FDA at 1-800-FDA-1088.

How should I store Moxifloxacin Hydrochloride?

•
Moxifloxacin Hydrochloride Tablets
o
Store Moxifloxacin Hydrochloride 59–86°F (15–30°C)
o
Keep Moxifloxacin Hydrochloride away from moisture (humidity)

Keep Moxifloxacin Hydrochloride and all medicines out of the reach of children.

General Information about Moxifloxacin Hydrochloride

•
Medicines are sometimes prescribed for purposes other than those listed in a Medication Guide. Do not use Moxifloxacin Hydrochloride for a condition for which it is not prescribed. Do not give Moxifloxacin Hydrochloride to other people, even if they have the same symptoms that you have. It may harm them.
•
This Medication Guide summarizes the most important information about Moxifloxacin Hydrochloride. If you would like more information about Moxifloxacin Hydrochloride, talk with your healthcare provider. You can ask your healthcare provider or pharmacist for information about Moxifloxacin Hydrochloride that is written for healthcare professionals. For more information call 1-866-770-3024.

What are the ingredients in Moxifloxacin Hydrochloride?

o
Active ingredient: moxifloxacin hydrochloride
o
Inactive ingredients: microcrystalline cellulose, lactose monohydrate, croscarmellose sodium, magnesium stearate, hypromellose, titanium dioxide, polyethylene glycol, and ferric oxide
Manufactured for:
Bayer HealthCare Pharmaceuticals Inc.
Whippany NJ, 07981

Moxifloxacin Hydrochloride Tablets manufactured in Germany

This Medication Guide has been approved by the U.S. Food and Drug Administration.

Distributed by:

Alvogen, Inc.
Pine Brook, NJ 07058 USA

Rx Only

©1999 Bayer HealthCare Pharmaceuticals Inc.

Revised 7/2016